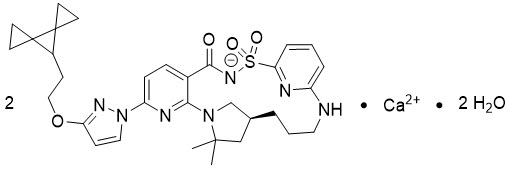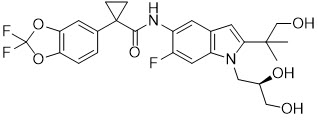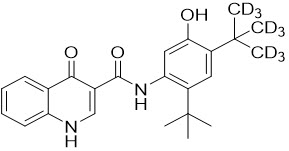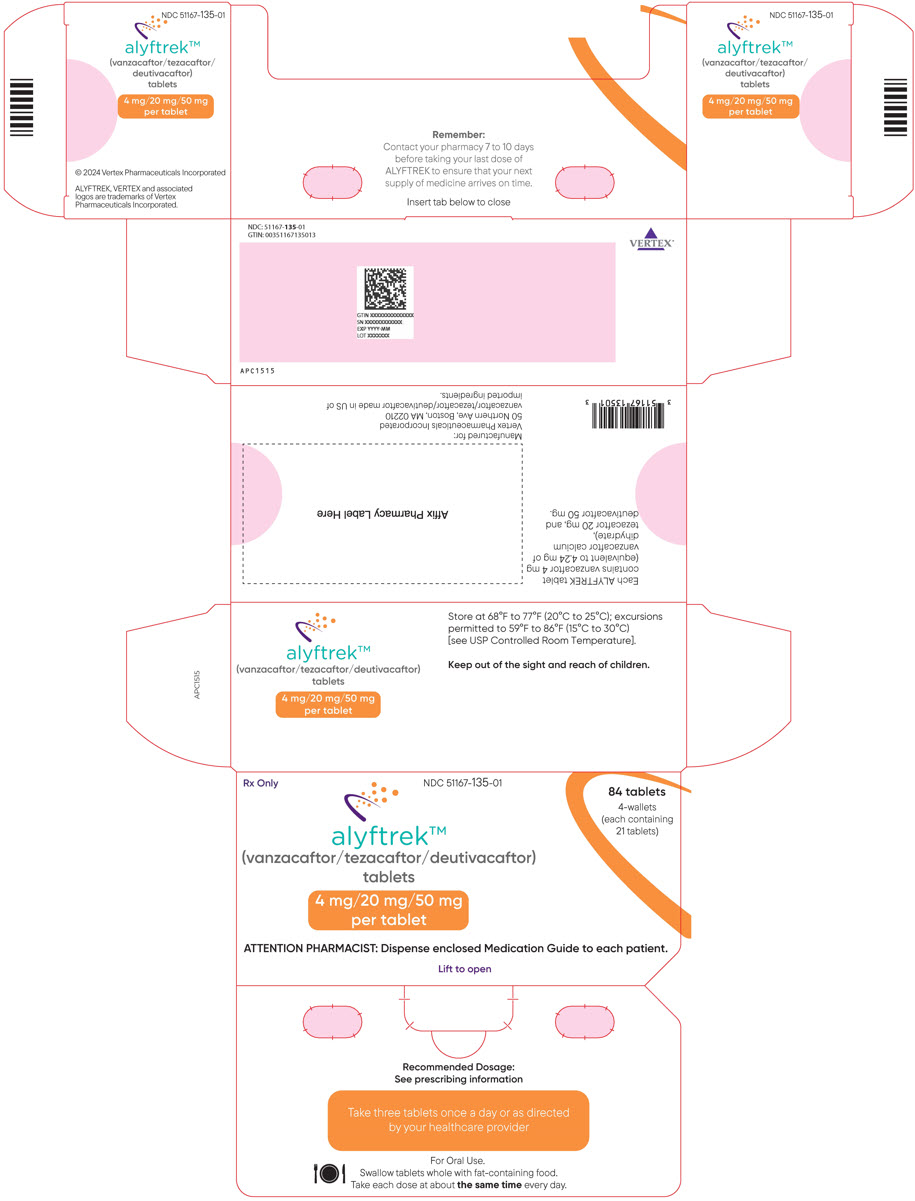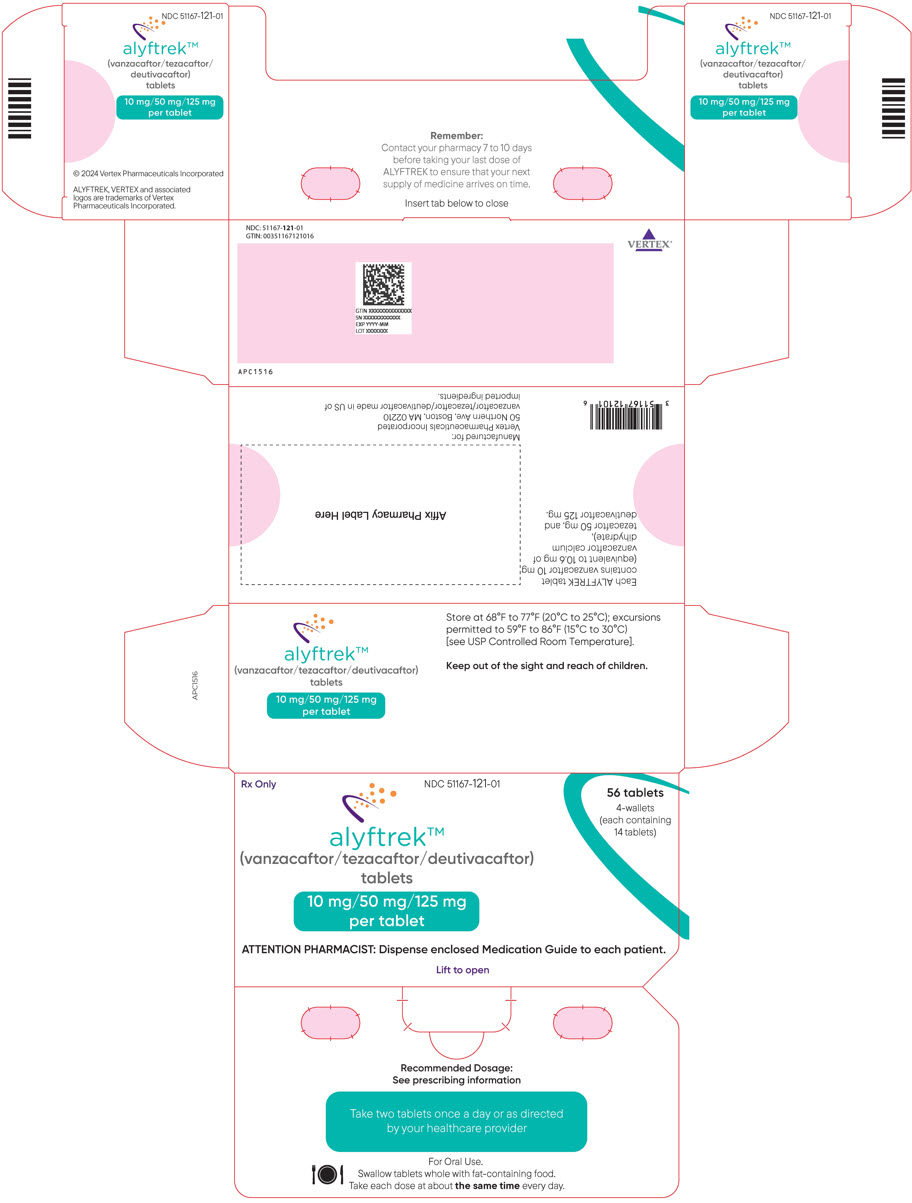 DRUG LABEL: ALYFTREK
NDC: 51167-135 | Form: TABLET, FILM COATED
Manufacturer: Vertex Pharmaceuticals Incorporated
Category: prescription | Type: HUMAN PRESCRIPTION DRUG LABEL
Date: 20250930

ACTIVE INGREDIENTS: vanzacaftor 4 mg/1 1; tezacaftor 20 mg/1 1; deutivacaftor 50 mg/1 1
INACTIVE INGREDIENTS: HYPROMELLOSE, UNSPECIFIED; HYPROMELLOSE ACETATE SUCCINATE 06081224 (3 MPA.S); Sodium lauryl sulfate; CROSCARMELLOSE SODIUM; Microcrystalline cellulose; Magnesium stearate; HYPROMELLOSE 2910 (15 MPA.S); HYDROXYPROPYL CELLULOSE, UNSPECIFIED; Titanium dioxide; Talc; FD&C BLUE NO. 1; FERRIC OXIDE RED

HIGHLIGHTS OF PRESCRIBING INFORMATION

These highlights do not include all the information needed to use ALYFTREK safely and effectively. See full prescribing information for ALYFTREK.
ALYFTREK (vanzacaftor, tezacaftor, and deutivacaftor tablets), for oral use
Initial U.S. Approval: 2024

WARNING: DRUG-INDUCED LIVER INJURY AND LIVER FAILURE

See full prescribing information for complete boxed warning.

- Elevated transaminases have been observed in patients treated with ALYFTREK (5.1, 6).
- Cases of serious and potentially fatal drug-induced liver injury and liver failure leading to transplantation and death were reported in patients who were taking ELX/TEZ/IVA, a drug containing the same or similar active ingredients as ALYFTREK (5.1).
- Assess liver function tests (ALT, AST, alkaline phosphatase, bilirubin) in all patients prior to initiating ALYFTREK, every month for first 6 months, every 3 months for next 12 months, then at least annually (2.1, 5.1).
- Interrupt ALYFTREK for significant elevations in LFTs or signs or symptoms of liver injury. Follow patients closely with clinical and laboratory monitoring until abnormalities resolve (5.1).
- Resume ALYFTREK if abnormalities resolve and only if the benefit is expected to outweigh the risk (5.1).
- ALYFTREK should not be used in patients with severe hepatic impairment (Child-Pugh Class C). ALYFTREK is not recommended in patients with moderate hepatic impairment (Child-Pugh Class B) (2.4, 5.1, 8.7, 12.3).

RECENT MAJOR CHANGES

Warnings and Precautions, Intracranial Hypertension (5.4) | 09/2025

1 INDICATIONS AND USAGE

ALYFTREK is a combination of deutivacaftor, a CFTR potentiator, tezacaftor, and vanzacaftor indicated for the treatment of cystic fibrosis (CF) in patients aged 6 years and older who have at least one F508del mutation or another responsive mutation in the CFTR gene. (1, 12.1)

If the patient's genotype is unknown, an FDA-cleared CF mutation test should be used to confirm the presence of at least one indicated mutation. (1, 12.1)

2 DOSAGE AND ADMINISTRATION

Prior to initiating ALYFTREK obtain liver function tests (ALT, AST, alkaline phosphatase, and bilirubin) in all patients. Monitor liver function tests every month during the first 6 months of treatment, then every 3 months during the next 12 months, then at least annually thereafter. (2.1, 5.1)

Recommended Dosage for Adult and Pediatric Patients Aged 6 Years and Older (with fat-containing food) (2.2)
Age | Weight | Once Daily Oral Dosage
6 to less than 12 years old | Less than 40 kg | Three tablets of vanzacaftor 4 mg/tezacaftor 20 mg/deutivacaftor 50 mg
6 to less than 12 years old | Greater than or equal to 40 kg | Two tablets of vanzacaftor 10 mg/tezacaftor 50 mg/deutivacaftor 125 mg
12 years and older | Any Weight | Two tablets of vanzacaftor 10 mg/tezacaftor 50 mg/deutivacaftor 125 mg

- Should not be used in patients with severe hepatic impairment. Use not recommended in patients with moderate hepatic impairment unless the benefit outweighs the risk. If used, no dose adjustment is recommended. Liver function tests should be closely monitored. (2.4, 5.1, 6.1, 8.7)
- See full prescribing information for dosage modifications for concomitant use of ALYFTREK with strong or moderate CYP3A inhibitors. (2.3, 5.6, 7.1)

3 DOSAGE FORMS AND STRENGTHS

Tablets:

- Fixed-dose combination containing vanzacaftor 4 mg, tezacaftor 20 mg, and deutivacaftor 50 mg. (3)
- Fixed-dose combination containing vanzacaftor 10 mg, tezacaftor 50 mg, and deutivacaftor 125 mg. (3)

4 CONTRAINDICATIONS

None. (4)

5 WARNINGS AND PRECAUTIONS

- Drug-Induced Liver Injury and Liver Failure: Elevated transaminases have been observed in patients treated with ALYFTREK. Cases of serious and potentially fatal drug-induced liver injury and liver failure have been reported with a drug that contains the same or similar active ingredients as ALYFTREK. Assess liver function tests (ALT, AST, alkaline phosphatase, and bilirubin) in all patients prior to initiating and throughout treatment with ALYFTREK. Interrupt ALYFTREK in the event of significant elevations in liver function tests or signs or symptoms of liver injury. ALYFTREK should not be used in patients with severe hepatic impairment (Child-Pugh Class C). ALYFTREK is not recommended in patients with moderate hepatic impairment (Child-Pugh Class B). (2.4, 5.1, 8.7)
- Hypersensitivity Reactions: Hypersensitivity reactions, including anaphylaxis, have been reported in the postmarketing setting for drugs containing elexacaftor, tezacaftor, and/or ivacaftor. If signs or symptoms of serious hypersensitivity reactions develop during ALYFTREK treatment, discontinue ALYFTREK and initiate appropriate therapy. (5.2)
- Patients Who Discontinued or Interrupted Elexacaftor-, Tezacaftor-, or Ivacaftor-Containing Drugs Due to Adverse Reactions: Consider benefits and risks before using ALYFTREK in patients who discontinued or interrupted elexacaftor-, tezacaftor-, or ivacaftor-containing drugs due to adverse reactions. If ALYFTREK is used, closely monitor for adverse reactions as clinically appropriate. (5.3)
- Intracranial hypertension: Intracranial hypertension (IH) has been reported in the postmarketing setting with use of drugs containing the same or similar active ingredients as ALYFTREK. If an unusual headache or visual disturbances occur during treatment, and IH is suspected, interrupt ALYFTREK and refer for prompt medical evaluation. (5.4)
- Reduced Effectiveness in Patients with Concomitant Use with CYP3A Inducers: Concomitant use with strong and moderate CYP3A inducers decreased vanzacaftor, tezacaftor, and deutivacaftor exposure, which may reduce ALYFTREK efficacy. Therefore, concomitant use is not recommended. (5.5, 7.1)
- Adverse Reactions with Concomitant Use with CYP3A Inhibitors: Concomitant use with strong or moderate CYP3A inhibitors increased vanzacaftor, tezacaftor, and deutivacaftor exposure, which may increase the risk of ALYFTREK associated adverse reactions. Reduce the ALYFTREK dosage with concomitant use. (2.3, 5.6, 7.1)
- Cataracts: Non-congenital lens opacities/cataracts have been reported in patients with CF aged 18 years or less treated with drugs containing ivacaftor. Baseline and follow up ophthalmological examinations are recommended in pediatric patients treated with ALYFTREK. (5.7, 8.4)

6 ADVERSE REACTIONS

Most common adverse reactions to ALYFTREK (≥5% of patients and at a frequency higher than ELX/TEZ/IVA by ≥1%) were cough, nasopharyngitis, upper respiratory tract infection, headache, oropharyngeal pain, influenza, fatigue, increased ALT, rash, increased AST, and sinus congestion. (6.1)

To report SUSPECTED ADVERSE REACTIONS, contact Vertex Pharmaceuticals Incorporated at 1-877-634-8789 or FDA at 1-800-FDA-1088 or www.fda.gov/medwatch.

7 DRUG INTERACTIONS

- Strong or moderate CYP3A inducers: Concomitant use with ALYFTREK is not recommended. (5.5, 7.1)
- Strong or moderate CYP3A inhibitors: Reduce ALYFTREK dosage with concomitant use. Avoid food or drink containing grapefruit. (2.3, 5.6, 7.1)

FULL PRESCRIBING INFORMATION

WARNING: DRUG-INDUCED LIVER INJURY AND LIVER FAILURE

Elevated transaminases have been observed in patients treated with ALYFTREK. Cases of serious and potentially fatal drug-induced liver injury and liver failure were reported in patients who were taking a fixed-dose combination drug containing elexacaftor, tezacaftor, and ivacaftor, which contains the same or similar active ingredients as ALYFTREK. Liver injury has been reported within the first month of therapy and up to 15 months following initiation of elexacaftor/tezacaftor/ivacaftor [see Warnings and Precautions (5.1) and Adverse Reactions (6)].

Assess liver function tests (ALT, AST, alkaline phosphatase, and bilirubin) in all patients prior to initiating ALYFTREK, every month during the first 6 months of treatment, then every 3 months for the next 12 months, then at least annually thereafter. Consider more frequent monitoring for patients with a history of liver disease or elevated liver function tests at baseline [see Dosage and Administration (2.1), Warnings and Precautions (5.1), Adverse Reactions (6), and Use in Specific Populations (8.7)].

Interrupt ALYFTREK for significant elevations in liver function tests or in the event of signs or symptoms of liver injury. Consider referral to a hepatologist. Follow patients closely with clinical and laboratory monitoring until abnormalities resolve. If abnormalities resolve, resume treatment only if the benefit is expected to outweigh the risk. Closer monitoring is advised after resuming ALYFTREK [see Warnings and Precautions (5.1)].

ALYFTREK should not be used in patients with severe hepatic impairment (Child-Pugh Class C). ALYFTREK is not recommended in patients with moderate hepatic impairment (Child-Pugh Class B) and should only be considered when there is a clear medical need, and the benefit outweighs the risk. If used, monitor patients closely [see Dosage and Administration (2.4), Warnings and Precautions (5.1), Adverse Reactions (6), Use in Specific Populations (8.7), and Clinical Pharmacology (12.3)].

1 INDICATIONS AND USAGE

ALYFTREK is indicated for the treatment of cystic fibrosis (CF) in patients 6 years of age and older who have at least one F508del mutation or another responsive mutation in the cystic fibrosis transmembrane conductance regulator (CFTR) gene (see Table 5) [see Clinical Pharmacology (12.1)].

If the patient's genotype is unknown, an FDA-cleared CF mutation test should be used to confirm the presence of at least one indicated mutation.

2 DOSAGE AND ADMINISTRATION

2.1 Recommended Laboratory Testing Prior to ALYFTREK Initiation and During Treatment

Prior to initiating ALYFTREK, obtain liver function tests (ALT, AST, alkaline phosphatase, and bilirubin) for all patients. Monitor liver function tests every month during the first 6 months of treatment, then every 3 months for the next 12 months, then at least annually thereafter. Consider more frequent monitoring for patients with a history of liver disease, elevated liver function tests at baseline, or a history of elevated liver function tests with drugs containing elexacaftor, tezacaftor, and/or ivacaftor [see Warnings and Precautions (5.1) and Use in Specific Populations (8.7)].

2.2 Recommended Dosage

The recommended ALYFTREK dosage in adult and pediatric patients aged 6 years and older is provided in Table 1. Administer ALYFTREK orally (swallow the tablets whole) with fat-containing food, once daily, at approximately the same time each day [see Clinical Pharmacology (12.3)]. Examples of meals or snacks that contain fat are those prepared with butter or oils or those containing eggs, peanut butter, cheeses, nuts, whole milk, or meats.

Table 1: Recommended Dosage of ALYFTREK in Adult and Pediatric Patients Aged 6 Years and Older
Age | Weight | Once Daily Oral Dosage
6 to less than 12 years old | Less than 40 kg | Three tablets of vanzacaftor 4 mg/tezacaftor 20 mg/deutivacaftor 50 mg (total dose of vanzacaftor 12 mg/tezacaftor 60 mg/ deutivacaftor 150 mg)
6 to less than 12 years old | Greater than or equal to 40 kg | Two tablets of vanzacaftor 10 mg/tezacaftor 50 mg/deutivacaftor 125 mg (total dose of vanzacaftor 20 mg/tezacaftor 100 mg/ deutivacaftor 250 mg)
12 years and older | Any weight | Two tablets of vanzacaftor 10 mg/tezacaftor 50 mg/deutivacaftor 125 mg (total dose of vanzacaftor 20 mg/tezacaftor 100 mg/ deutivacaftor 250 mg)

2.3 Dosage Modification for Strong or Moderate CYP3A Inhibitors

Table 2 describes the recommended dosage modification for ALYFTREK when used concomitantly with strong or moderate CYP3A inhibitors [see Warnings and Precautions (5.6)]. Administer ALYFTREK orally (swallow the tablets whole) with fat-containing food, once daily, at approximately the same time each day [see Clinical Pharmacology (12.3)].

Table 2: Dosage Modification for Concomitant Use of ALYFTREK with Strong or Moderate CYP3A Inhibitors in Adult and Pediatric Patients Aged 6 Years and Older
Age | Weight | Moderate CYP3A Inhibitors | Strong CYP3A Inhibitors
6 to less than 12 years old | Less than 40 kg | Two tablets of vanzacaftor 4 mg/tezacaftor 20 mg/deutivacaftor 50 mg every other day (total dose of vanzacaftor 8 mg/tezacaftor 40 mg/deutivacaftor 100 mg) | Two tablets of vanzacaftor 4 mg/tezacaftor 20 mg/deutivacaftor 50 mg once a week (total dose of vanzacaftor 8 mg/tezacaftor 40 mg/deutivacaftor 100 mg)
6 to less than 12 years old | Greater than or equal to 40 kg | One tablet of vanzacaftor 10 mg/tezacaftor 50 mg/deutivacaftor 125 mg every other day | One tablet of vanzacaftor 10 mg/tezacaftor 50 mg/deutivacaftor 125 mg once a week
12 years and older | Any weight | One tablet of vanzacaftor 10 mg/tezacaftor 50 mg/deutivacaftor 125 mg every other day | One tablet of vanzacaftor 10 mg/tezacaftor 50 mg/deutivacaftor 125 mg once a week

2.4 Recommended Dosage for Patients with Hepatic Impairment

- Severe Hepatic Impairment (Child-Pugh Class C): ALYFTREK should not be used in patients with severe hepatic impairment (HI) (Child-Pugh Class C).
- Moderate Hepatic Impairment (Child-Pugh Class B): The use of ALYFTREK in patients with moderate HI (Child-Pugh Class B) is not recommended. Use of ALYFTREK should only be considered in patients with moderate HI when there is a clear medical need, and the benefit outweighs the risk. If used, the recommended dosage in patients with moderate HI is the same as for patients with normal hepatic function. Liver function tests should be closely monitored [see Dosage and Administration (2.1, 2.2)].
- Mild Hepatic Impairment (Child-Pugh Class A): The recommended dosage of ALYFTREK in patients with mild HI (Child-Pugh Class A) is the same as in patients with normal hepatic function. Liver function tests should be closely monitored [see Dosage and Administration (2.1, 2.2)].

2.5 Recommendations Regarding Missed Dose(s)

If 6 hours or less have passed since the missed dose, take the missed dose as soon as possible and continue on the original schedule.

If more than 6 hours have passed since the missed dose, skip the missed dose, and continue on the original schedule the next day.

3 DOSAGE FORMS AND STRENGTHS

Tablets:

- Fixed-dose combination containing vanzacaftor 4 mg (equivalent to 4.24 mg of vanzacaftor calcium dihydrate), tezacaftor 20 mg, and deutivacaftor 50 mg. Each tablet is purple, round-shaped, film-coated, debossed with "V4" on one side and plain on the other.
- Fixed-dose combination containing vanzacaftor 10 mg (equivalent to 10.6 mg of vanzacaftor calcium dihydrate), tezacaftor 50 mg, and deutivacaftor 125 mg. Each tablet is purple, oblong-shaped, film-coated, debossed with "V10" on one side and plain on the other.

4 CONTRAINDICATIONS

None.

5 WARNINGS AND PRECAUTIONS

5.1 Drug-Induced Liver Injury and Liver Failure

Elevated transaminases have been observed in patients treated with ALYFTREK [Adverse Reactions (6.1)]. Cases of serious and potentially fatal drug-induced liver injury and liver failure have been reported in patients with and without a history of liver disease who were taking a fixed-dose combination drug containing elexacaftor, tezacaftor, and ivacaftor (ELX/TEZ/IVA), which contains the same or similar active ingredients as ALYFTREK. Liver injury has been reported within the first month of therapy and up to 15 months following initiation of ELX/TEZ/IVA.

Assess liver function tests (ALT, AST, alkaline phosphatase, and bilirubin) in all patients prior to initiating ALYFTREK. Assess liver function tests every month during the first 6 months of treatment, then every 3 months for the next 12 months, then at least annually thereafter. Consider more frequent monitoring in patients with a history of liver disease, elevated liver function tests at baseline, or a history of elevated liver function tests with drugs containing ELX, TEZ and/or IVA. [see Dosage and Administration (2.4) and Use in Specific Populations (8.7)].

Interrupt ALYFTREK in the event of signs or symptoms of liver injury. These may include:

- Significant elevations in liver function tests (e.g., ALT or AST >5× the upper limit of normal (ULN) or ALT or AST >3× ULN with bilirubin >2× ULN)
- Clinical signs or symptoms suggestive of liver injury (e.g., jaundice, right upper quadrant pain, nausea, vomiting, altered mental status, ascites)

Consider referral to a hepatologist and follow patients closely with clinical and laboratory monitoring until abnormalities resolve. If abnormalities resolve and if the benefit is expected to outweigh the risk, resume ALYFTREK treatment with close monitoring.

ALYFTREK should not be used in patients with severe hepatic impairment (Child-Pugh Class C). ALYFTREK is not recommended in patients with moderate hepatic impairment (Child-Pugh Class B) and should only be considered when there is a clear medical need, and the benefit outweighs the risk. If used, monitor patients closely [see Dosage and Administration (2.4), Use in Specific Populations (8.7), and Clinical Pharmacology (12.3)].

5.2 Hypersensitivity Reactions, Including Anaphylaxis

Hypersensitivity reactions, including cases of anaphylaxis, have been reported in the postmarketing setting of drugs containing ELX, TEZ, and/or IVA (the same or similar active ingredients in ALYFTREK). If signs or symptoms of serious hypersensitivity reactions develop during ALYFTREK treatment, discontinue ALYFTREK and institute appropriate therapy. Consider the benefits and risks for the individual patient to determine whether to resume treatment with ALYFTREK.

5.3 Patients Who Discontinued or Interrupted Elexacaftor-, Tezacaftor-, or Ivacaftor-Containing Drugs Due to Adverse Reactions

There are no available safety data for ALYFTREK in patients who previously discontinued or interrupted treatment with drugs containing elexacaftor, tezacaftor, or ivacaftor due to adverse reactions. Consider the benefits and risks before using ALYFTREK in these patients. If ALYFTREK is used in these patients, closely monitor for adverse reactions as clinically appropriate.

5.4 Intracranial Hypertension

Cases of intracranial hypertension (IH) have been reported in the postmarketing setting with the use of drugs containing the same or similar active ingredients as ALYFTREK [see Adverse Reactions (6.2)]. Clinical manifestations of IH include headache, blurred vision, diplopia, and potential vision loss; papilledema can be found on fundoscopy. If an unusual headache or visual disturbances occur during treatment, and IH is suspected, interrupt ALYFTREK and refer for prompt medical evaluation. Consider the benefits and risks for the individual patient to determine whether to resume treatment with ALYFTREK. Patients should be monitored until IH resolution and for recurrence. Patients with elevated vitamin A levels may be at increased risk.

5.5 Reduced Effectiveness with Concomitant Use with CYP3A Inducers

Following concomitant use of strong or moderate CYP3A inducers with ALYFTREK, exposures of vanzacaftor, tezacaftor, and deutivacaftor were decreased, which may reduce ALYFTREK effectiveness. Concomitant use with strong or moderate CYP3A inducers is not recommended [see Drug Interactions (7.1)].

5.6 Adverse Reactions with Concomitant Use with CYP3A Inhibitors

Following concomitant use of strong or moderate CYP3A inhibitors with ALYFTREK, exposures of vanzacaftor, tezacaftor, and deutivacaftor were increased, which may increase the risk of ALYFTREK-associated adverse reactions. Reduce the ALYFTREK dosage with concomitant use of strong or moderate CYP3A inhibitors [see Dosage and Administration (2.3) and Drug Interactions (7.1)].

5.7 Cataracts

Cases of non-congenital lens opacities have been reported in pediatric patients treated with drugs containing ivacaftor (which is similar to an active ingredient in ALYFTREK). Although other risk factors were present (such as corticosteroid use, exposure to radiation) in some cases, a possible risk attributable to ivacaftor treatment cannot be excluded. Baseline and follow-up ophthalmological examinations are recommended in pediatric patients treated with ALYFTREK [see Use in Specific Populations (8.4)].

6 ADVERSE REACTIONS

The following clinically significant adverse reactions are discussed in greater detail in other sections of the labeling:

- Drug-Induced Liver Injury and Liver Failure [see Warnings and Precautions (5.1)]
- Hypersensitivity Reactions, Including Anaphylaxis [see Warnings and Precautions (5.2)]
- Patients Who Discontinued or Interrupted Elexacaftor-, Tezacaftor-, or Ivacaftor-Containing Drugs Due to Adverse Reactions [see Warnings and Precautions (5.3)]
- Intracranial Hypertension [see Warnings and Precautions (5.4)]
- Cataracts [see Warnings and Precautions (5.7)]

6.1 Clinical Trials Experience

Because clinical trials are conducted under widely varying conditions, adverse reaction rates observed in the clinical trials of a drug cannot be directly compared to rates in the clinical trials of another drug and may not reflect the rates observed in clinical practice.

The adverse reactions data below are from clinical trials of ALYFTREK in patients 6 years of age and older with CF with at least one responsive CFTR mutation who were able to tolerate ELX/TEZ/IVA. Adverse reactions data in patients who previously discontinued or interrupted ELX/TEZ/IVA due to adverse reactions are not available.

Adverse Reactions in Patients Aged 12 Years and Older with CF

The safety of ALYFTREK is based on 480 patients with CF aged 12 years and older who have at least one F508del mutation or another responsive mutation in the CFTR gene in two, 52-week, active-controlled trials (Trials 1 and 2) [see Clinical Studies (14)]. In both trials, patients received a fixed-dose combination drug containing elexacaftor, tezacaftor, and ivacaftor (ELX/TEZ/IVA) in a 4-week run-in period and then were subsequently randomized to continue ELX/TEZ/IVA (elexacaftor 200 mg/tezacaftor 100 mg/ivacaftor 150 mg in the morning and ivacaftor 150 mg in the evening) or receive ALYFTREK (vanzacaftor 20 mg/tezacaftor 100 mg/deutivacaftor 250 mg) once daily. Patients with a history of prior intolerance to ELX/TEZ/IVA (i.e., patients who discontinued or interrupted treatment due to adverse reactions) were excluded. Trials 1 and 2 were not designed to evaluate meaningful comparisons of the incidence of adverse reactions between the ALYFTREK and ELX/TEZ/IVA treatment groups. For additional information regarding ELX/TEZ/IVA adverse reactions, refer to ELX/TEZ/IVA Prescribing Information.

In Trial 1 and Trial 2 combined, the proportion of patients who discontinued treatment prematurely due to adverse reactions were 3.8% and 3.7% in ALYFTREK and ELX/TEZ/IVA treatment groups, respectively.

Serious adverse reactions that occurred more frequently with ALYFTREK treatment than with ELX/TEZ/IVA treatment that occurred in 2 or more patients (≥0.4%) were influenza (1.5%), increased AST (0.4%), increased GGT (0.4%), depression (0.4%), and syncope (0.4%).

Table 3: Adverse Reactions Occurring in ≥5% of ALYFTREK-Treated Patients and ≥1% Higher than ELX/TEZ/IVA-Treated Patients Aged 12 Years and Older with CF Who Had at Least One F508del Mutation or Responsive Mutation in the CFTR Gene (Trials 1 and 2)
Adverse Reactions | ALYFTREK N=480 | ELX/TEZ/IVA N=491
Cough [Cough is composed of several similar terms including productive cough.] | 120 (25%) | 116 (24%)
Nasopharyngitis | 102 (21%) | 95 (19%)
Upper respiratory tract infection [Upper respiratory tract infection is composed of several similar terms including viral upper respiratory tract infection.] | 101 (21%) | 97 (20%)
Headache | 76 (16%) | 63 (13%)
Oropharyngeal pain | 69 (14%) | 60 (12%)
Influenza | 52 (11%) | 26 (5%)
Fatigue | 51 (11%) | 46 (9%)
ALT increased | 38 (8%) | 29 (6%)
Rash | 37 (8%) | 22 (4%)
AST increased | 33 (7%) | 27 (5%)
Sinus congestion | 32 (7%) | 15 (3%)
Abbreviations: ALT, alanine aminotransferase; AST, aspartate aminotransferase; ELX, elexacaftor; IVA, ivacaftor; TEZ, tezacaftor

Adverse events that occurred in ≥5% of ELX/TEZ/IVA-treated patients at a similar or higher incidence than the ALYFTREK-treated patients included: infective pulmonary exacerbation of CF, COVID-19, diarrhea, abdominal pain, pyrexia, nasal congestion, increased sputum, increased blood creatinine phosphokinase, rhinorrhea, hemoptysis, nausea, back pain, arthralgia, constipation, sinusitis, dyspnea, and vomiting.

Liver Function Test Elevations

The incidence of adverse reactions of transaminase elevations was 9% in ALYFTREK-treated patients and 7.1% in ELX/TEZ/IVA-treated patients in Trials 1 and 2. In these trials, 1.5% of ALYFTREK-treated patients and 0.6% of ELX/TEZ/IVA-treated patients discontinued treatment for elevated transaminases. Table 4 shows the incidence of maximum transaminase (ALT or AST) elevations in Trials 1 and 2.

Table 4: Number and Incidence of Maximum Transaminase Elevation in Patients Aged 12 Years and Older with CF Who Had at Least One F508del Mutation or Responsive Mutation in the CFTR Gene (Trials 1 and 2)
Maximum ALT or AST Elevation | ALYFTREK N=480 | ELX/TEZ/IVA [Trials 1 and 2 were not designed to evaluate meaningful comparisons of safety between the ALYFTREK and ELX/TEZ/IVA treatment groups. For additional information regarding ELX/TEZ/IVA transaminase elevations, refer to ELX/TEZ/IVA Prescribing Information.] N=491
>3× ULN | 29 (6%) | 15 (3.1%)
>5× ULN | 12 (2.5%) | 6 (1.2%)
>8× ULN | 6 (1.3%) | 1 (0.2%)
Abbreviations: ALT: alanine aminotransferase; AST, aspartate aminotransferase; ELX, elexacaftor; IVA, ivacaftor; TEZ, tezacaftor.

Rash

In Trials 1 and 2, the incidence of rash (e.g., rash, rash pruritic) was 11% in ALYFTREK-treated patients and 7.7% in ELX/TEZ/IVA-treated patients. The rashes were generally mild to moderate in severity. The incidence of rash was 9.4% in males and 13% in females with ALYFTREK treatment and 7.6% in males and 7.9% in females with ELX/TEZ/IVA treatment. A role of hormonal contraceptives in the occurrence of rash cannot be excluded [see Drug Interactions (7.3)].

Increased Creatine Phosphokinase

In Trials 1 and 2, the incidence of maximum creatine phosphokinase >5× the ULN was 7.9% with ALYFTREK treatment and 6.5% with ELX/TEZ/IVA treatment. Discontinuation due to increased creatinine phosphokinase was 0.2% for ALYFTREK-treated patients and 0.2% for ELX/TEZ/IVA-treated patients. Cases of rhabdomyolysis without renal involvement have been reported in patients who had recently exercised taking a fixed-dose combination drug containing ELX/TEZ/IVA (the same or similar active ingredients as ALYFTREK).

Increased Blood Pressure

Elevations in mean systolic and diastolic blood pressure have been reported in patients taking a fixed-dose combination drug containing ELX/TEZ/IVA (the same or similar active ingredients as ALYFTREK). The proportion of patients who had systolic blood pressure >140 mmHg and >10 mmHg increase from baseline on at least two occasions was 3.5% in ALYFTREK-treated patients and 3.3% in ELX/TEZ/IVA-treated patients. The proportion of patients who had diastolic blood pressure >90 mmHg and >5 mmHg increase from baseline on at least two occasions was 1.7% in ALYFTREK-treated patients and 1.8% in ELX/TEZ/IVA-treated patients. The mean systolic and diastolic blood pressures remained in the normal range from both ALYFTREK and ELX/TEZ/IVA treatment arms.

Adverse Reactions in Pediatric Patients Aged 6 to Less Than 12 Years with CF

A 24-week, open-label trial of ALYFTREK was conducted in 78 patients with CF aged 6 to less than 12 years with at least one mutation responsive to ELX/TEZ/IVA (Trial 3). In Trial 3, patients who weighed less than 40 kg received ALYFTREK (vanzacaftor 12 mg/tezacaftor 60 mg/deutivacaftor 150 mg once daily) and patients who weighed 40 kg or more received ALYFTREK (vanzacaftor 20 mg/tezacaftor 100 mg/deutivacaftor 250 mg once daily). Adverse reactions for these patients were generally similar to those reported in Trial 1 and Trial 2. In Trial 3, the incidence of maximum transaminase (ALT or AST) >3×, >5×, and >8× ULN were 3.8%, 1.3%, and 0%, respectively.

6.2 Postmarketing Experience

Postmarketing Adverse Reactions with Other Drugs Containing the Same or Similar Active Ingredients as ALYFTREK

The following adverse reactions have been identified during post approval use of drugs containing the same or similar active ingredients as ALYFTREK. Because these reactions are reported voluntarily from a population of uncertain size, it is not always possible to reliably estimate their frequency or establish a causal relationship to drug exposure.

Nervous System Disorders: intracranial hypertension

7 DRUG INTERACTIONS

7.1 Effect of Other Drugs and Grapefruit on ALYFTREK

Strong or Moderate CYP3A Inducers

Concomitant use of ALYFTREK with strong or moderate CYP3A inducers is not recommended.

Vanzacaftor, tezacaftor, and deutivacaftor are substrates of CYP3A. Concomitant use of ALYFTREK with a strong or moderate CYP3A inducer decreases vanzacaftor, tezacaftor, and deutivacaftor exposure [see Clinical Pharmacology (12.3)] which may reduce ALYFTREK effectiveness [see Warnings and Precautions (5.5)].

Strong or Moderate CYP3A Inhibitors

Reduce the ALYFTREK dosage when used concomitantly with a strong or moderate CYP3A inhibitor [see Dosage and Administration (2.3)].

Vanzacaftor, tezacaftor, and deutivacaftor are CYP3A substrates. Concomitant use with a strong CYP3A inhibitor increases vanzacaftor, tezacaftor, and deutivacaftor exposure [see Clinical Pharmacology (12.3)], which may increase the risk of ALYFTREK adverse reactions [see Warnings and Precautions (5.6)]. Concomitant use with a moderate CYP3A inhibitor is predicted to increase vanzacaftor, tezacaftor, and deutivacaftor exposure [see Clinical Pharmacology (12.3)], which may increase the risk of ALYFTREK adverse reactions [see Warnings and Precautions (5.6)].

Grapefruit

Food or drink containing grapefruit should be avoided during treatment with ALYFTREK. Concomitant use of ALYFTREK with grapefruit juice which contains one or more components that moderately inhibit CYP3A may increase exposure of vanzacaftor, tezacaftor and deutivacaftor.

7.2 Effect of ALYFTREK on Other Drugs

P-glycoprotein (P-gp) Substrates

Unless otherwise recommended in the P-gp substrate Prescribing Information, monitor more frequently for adverse reactions with concomitant use of ALYFTREK with P-gp substrates where minimal concentration changes may lead to serious adverse reactions related to P-gp substrates.

Tezacaftor and deutivacaftor (components of ALYFTREK) are P-gp inhibitors. Administration of tezacaftor/ivacaftor increases exposure of P-gp substrates [see Clinical Pharmacology (12.3)], which may increase the risk of adverse reactions related to these substrates.

Breast Cancer Resistance Protein (BCRP) Substrates

Unless otherwise recommended in BCRP substrate Prescribing Information, monitor more frequently for adverse reactions with concomitant use of ALYFTREK with BCRP substrate where minimal concentrations may lead to serious adverse reactions related to BCRP substrates.

Vanzacaftor (VNZ) and deutivacaftor (D-IVA) (components of ALYFTREK) are inhibitors of BCRP in vitro. Concomitant use of ALYFTREK with BCRP substrates may increase exposure of these substrates; however, this has not been studied clinically [see Clinical Pharmacology (12.3)].

CYP2C9 Substrates

Use caution when ALYFTREK is used concomitantly with CYP2C9 substrates. Monitor the international normalized ratio (INR) more frequently with concomitant use of ALYFTREK with warfarin.

This recommendation is based upon a mechanistic understanding of deutivacaftor pharmacokinetics (it is an inhibitor of CYP2C9 in vitro) [see Clinical Pharmacology (12.3)]. Concomitant use of ALYFTREK with CYP2C9 substrates may increase exposure of these substrates; however, this has not been studied clinically.

7.3 Drugs with No Clinically Significant Interactions with ALYFTREK

Ciprofloxacin

No clinically relevant effect on the exposure of tezacaftor was observed when tezacaftor/ivacaftor was used concomitantly with ciprofloxacin [see Clinical Pharmacology (12.3)].

Hormonal Contraceptives

No clinically significant differences in the pharmacokinetics of ethinyl estradiol/norethindrone containing hormonal contraceptives were observed when used concomitantly with tezacaftor in combination with ivacaftor and ivacaftor alone [see Clinical Pharmacology (12.3)]. No clinically significant differences in the pharmacokinetics of ethinyl estradiol/norethindrone containing hormonal contraceptives are expected when used in combination with ALYFTREK based upon a mechanistic understanding of vanzacaftor, tezacaftor, and deutivacaftor pharmacokinetics [see Clinical Pharmacology (12.3)]; however, this has not been studied clinically.

A role for hormonal contraceptives contributing to rash cannot be excluded [see Adverse Reactions (6.1)]. For patients with CF taking hormonal contraceptives who develop rash, consider interrupting ALYFTREK and hormonal contraceptives. Following the resolution of rash, consider resuming ALYFTREK without the hormonal contraceptives. If rash does not recur, resumption of hormonal contraceptives can be considered.

8 USE IN SPECIFIC POPULATIONS

8.1 Pregnancy

Risk Summary

There are no available data on ALYFTREK use in pregnant women to evaluate for a drug-associated risk of major birth defects, miscarriage, or other adverse maternal or fetal outcomes. Although there are no animal reproduction studies with the concomitant administration of vanzacaftor, tezacaftor, and deutivacaftor, separate reproductive and developmental studies were conducted with vanzacaftor and tezacaftor in pregnant rats and rabbits. Deutivacaftor is a deuterated isotopologue of ivacaftor with a toxicity profile similar to ivacaftor. Reproductive and development studies were conducted with ivacaftor in pregnant rats and rabbits.

In animal embryo fetal development (EFD) studies, oral administration of vanzacaftor to pregnant rats and rabbits during organogenesis demonstrated no adverse developmental effects at doses that produced maternal exposures up to approximately 30 times the exposure at the maximum recommended human dose (MRHD) in rats and 22 times the MRHD in rabbits. Oral administration of tezacaftor to pregnant rats and rabbits during organogenesis demonstrated no adverse developmental effects at doses that produced maternal exposures up to approximately 3 times the exposure at the MRHD in rats and 0.2 times the MRHD in rabbits (based on summed AUCs of tezacaftor and the metabolite M1-TEZ). Oral administration of ivacaftor to pregnant rats and rabbits during organogenesis demonstrated no adverse developmental effects at doses that produced maternal exposures up to approximately 8 and 9 times the exposure at the MRHD, respectively (based on AUC of ivacaftor for rats and rabbits). No adverse developmental effects were observed after oral administration of vanzacaftor, tezacaftor, or ivacaftor to pregnant rats from the period of organogenesis through lactation at doses that produced maternal exposures approximately 18 times, 1 time, and 8 times the exposures at the MRHD, respectively (based on AUCs of vanzacaftor, tezacaftor and M1-TEZ, and ivacaftor) (see Data).

The estimated background risk of major birth defects and miscarriage for the indicated population is unknown. All pregnancies have a background risk of birth defect, loss, or other adverse outcomes. In the U.S. general population, the estimated background risk of major birth defects and miscarriage in clinically recognized pregnancies is 2% to 4% and 15% to 20%, respectively.

Data

Animal Data

Vanzacaftor: In an EFD study, pregnant rats were administered vanzacaftor at oral doses of 2.5, 5, and 10 mg/kg/day during the period of organogenesis from gestation Days 6-17. Vanzacaftor did not cause adverse effects to the fetus at exposures up to 30 times the MRHD (based on AUC for vanzacaftor at maternal doses up to 10 mg/kg/day). In an EFD study, pregnant rabbits were administered vanzacaftor at oral doses of 10, 40, and 70 mg/kg/day during the period of organogenesis from gestation Days 7-20. Vanzacaftor did not cause adverse effects to the fetus at exposures up to 22 times the MRHD (based on AUC of vanzacaftor at maternal doses up to 40 mg/kg/day). The high dose of 70 mg/kg/day (71 times the exposure at the MRHD) produced maternal toxicity (i.e., mortality, abortion, decreased mean body weight or body weight gains) and was associated with findings of increased post-implantation loss, decreased live fetuses, decreased fetal body weight, and increased kidney malformations. In a pre- and postnatal development (PPND) study in pregnant rats administered vanzacaftor at oral doses of 2.5, 5, and 10 mg/kg/day from gestation Day 6 through lactation Day 18, vanzacaftor did not cause adverse developmental effects in pups at maternal doses up to 10 mg/kg/day (approximately 18 times the exposure at the MRHD). Placental transfer of vanzacaftor was observed in pregnant rats.

Tezacaftor: In an EFD study, pregnant rats were administered tezacaftor at oral doses of 25, 50, and 100 mg/kg/day during the period of organogenesis from gestation Days 6-17. Tezacaftor did not cause adverse effects to the fetus at exposures up to 3 times the MRHD (based on summed AUCs of tezacaftor and M1-TEZ). Maternal toxicity in rats was observed at ≥50 mg/kg/day (approximately ≥1 time the MRHD). In an EFD study, pregnant rabbits were administered tezacaftor at oral doses of 10, 25, and 50 mg/kg/day during the period of organogenesis from gestation Days 7-20. Tezacaftor did not cause adverse effects to the fetus at exposures up to 0.2 times the MRHD (based on summed AUCs of tezacaftor and M1-TEZ). Lower fetal body weights were observed in rabbits at a maternally toxic dose that produced exposures approximately 1 time the MRHD (based on summed AUCs of tezacaftor and M1-TEZ at a maternal dose of 50 mg/kg/day). In a PPND study, pregnant rats were administered tezacaftor at oral doses of 25, 50, and 100 mg/kg/day from gestation Day 6 through lactation Day 18. Tezacaftor had no adverse developmental effects on pups at an exposure of approximately 1 time the MRHD (based on summed AUCs for tezacaftor and M1-TEZ at a maternal dose of 25 mg/kg/day). Decreased fetal body weights and early developmental delays in pinna detachment, eye opening, and righting reflex occurred at a maternally toxic dose (based on maternal weight loss) that produced exposures approximately 2 times the exposure at the MRHD (based on summed AUCs for tezacaftor and M1-TEZ). Placental transfer of tezacaftor was observed in pregnant rats.

Deutivacaftor: Animal reproduction studies have not been conducted with deutivacaftor. However, as a deuterated isotopologue of ivacaftor with a toxicity profile similar to ivacaftor based on a 13-week single-agent repeat dose toxicity study, the reproductive and developmental toxicity data from ivacaftor can inform the developmental and reproductive risks associated with deutivacaftor.

In an EFD study, pregnant rats were administered ivacaftor at oral doses of 50, 100, and 200 mg/kg/day during the period of organogenesis from gestation Days 7-17. Ivacaftor did not cause adverse effects to the fetus at exposures up to 8 times the MRHD for deutivacaftor (based on AUC of ivacaftor in animal studies up to 200 mg/kg/day). In an EFD study, pregnant rabbits were administered ivacaftor at oral doses of 25, 50, and 100 mg/kg/day during the period of organogenesis from gestation Days 7-19. Ivacaftor did not cause adverse effects to the fetus at exposures up to 9 times the MRHD for deutivacaftor (based on AUC of ivacaftor in animal studies). Maternal toxicity (i.e., death, decreased food consumption, decreased mean body weight and body weight gain, decreased clinical condition, abortions) was observed at doses greater than or equal to 50 mg/kg/day (approximately 3 times the MRHD). In a PPND study, pregnant rats were administered ivacaftor at oral doses of 50, 100, and 200 mg/kg/day from gestation Day 7 through lactation Day 20. Ivacaftor had no effects on delivery or growth and development of offspring at exposures up to 8 times the MRHD (based on AUC for ivacaftor at maternal oral doses up to 100 mg/kg/day). Decreased fetal body weights were observed at a maternally toxic dose (200 mg/kg/day, 13 times the exposure at MHRD). Placental transfer of ivacaftor was observed in pregnant rats and rabbits.

8.2 Lactation

Risk Summary

There are no data on the presence of vanzacaftor, tezacaftor, or deutivacaftor or their metabolites in human milk, the effects on the breastfed infant, or the effects on milk production.

Vanzacaftor and tezacaftor are excreted into the milk of lactating female rats. Deutivacaftor has not been evaluated; however, ivacaftor is excreted into the milk of lactating female rats (see Data). When a drug is present in animal milk, it is likely that the drug will be present in human milk. The developmental and health benefits of breastfeeding should be considered along with the mother's clinical need for ALYFTREK and any potential adverse effects on the breastfed child from ALYFTREK or from the underlying maternal condition.

Data

The concentration of vanzacaftor, tezacaftor, or deutivacaftor in animal milk does not necessarily predict the concentration of drug in human milk.

Vanzacaftor: Lacteal excretion of vanzacaftor in rats was demonstrated following a single oral dose (10 mg/kg) of ^14C-vanzacaftor administered 6 to 10 days postpartum to lactating dams. Exposure of ^14C-vanzacaftor in milk was approximately 0.2 times the value observed in plasma (based on AUC0-72h).

Tezacaftor: Lacteal excretion of tezacaftor in rats was demonstrated following a single oral dose (30 mg/kg) of ^14C-tezacaftor administered 6 to 10 days postpartum to lactating dams. Exposure of ^14C-tezacaftor in milk was approximately 3.0 times higher than in plasma (based on AUC0-72h).

Deutivacaftor: Deutivacaftor has not been evaluated; however, ivacaftor is excreted into the milk of lactating female rats. Lacteal excretion of ivacaftor in rats was demonstrated following a single oral dose (100 mg/kg) of ^14C-ivacaftor administered 9 to 10 days postpartum to lactating dams. Exposure of ^14C-ivacaftor in milk was approximately 1.5 times higher than in plasma (based on AUC0-24h).

8.4 Pediatric Use

The safety and effectiveness of ALYFTREK for the treatment of CF in pediatric patients aged 6 years and older who have at least one F508del mutation or another responsive mutation in the CFTR gene have been established. Use of ALYFTREK for this indication was supported by evidence from two adequate and well-controlled trials (Trials 1 and 2) in patients with CF aged 12 years and older who had at least one F508del mutation or another responsive mutation in the CFTR gene and additional pharmacokinetic and safety data in pediatric patients with CF aged 6 to less than 12 years who had at least one F508del mutation or another responsive mutation in the CFTR gene (Trial 3). In these trials, a total of 145 patients with CF aged 6 to less than 18 years received ALYFTREK including:

- In Trial 1, 26 adolescents aged 12 to less than 18 years who were heterozygous for F508del and a CFTR mutation that is not responsive to ivacaftor or tezacaftor/ivacaftor (minimal function mutation) [see Adverse Reactions (6.1) and Clinical Studies (14)].
- In Trial 2, 41 adolescents aged 12 to less than 18 years who were homozygous for F508del mutation, heterozygous for F508del mutation and either a gating or a residual function mutation, or with at least one mutation responsive to ELX/TEZ/IVA with no F508del mutation [see Adverse Reactions (6.1) and Clinical Studies (14)].
- In Trial 3, 78 pediatric patients with CF aged 6 to less than 12 years (mean age 9.1 years) with at least one mutation that is responsive to ELX/TEZ/IVA [see Adverse Reactions (6.1)]. In Trial 3, patients who weighed less than 40 kg patients received ALYFTREK (vanzacaftor 12 mg/tezacaftor 60 mg/deutivacaftor 150 mg once daily) and patients who weighed 40 kg or more received ALYFTREK (vanzacaftor 20 mg/tezacaftor 100 mg/deutivacaftor 250 mg once daily).

The efficacy of ALYFTREK in patients aged 6 to less than 12 years for this indication was extrapolated from patients aged 12 years and older with support from population pharmacokinetic analyses showing vanzacaftor, tezacaftor, and deutivacaftor exposure levels in patients aged 6 to less than 12 years to be within the range of exposures observed in patients aged 12 years and older [see Clinical Pharmacology (12.3)].

Safety of ALYFTREK in patients aged 6 to less than 12 years for this indication was based on Trial 3. The overall safety profile of patients in Trial 3 was generally similar to the safety data in adult and pediatric patients 12 years of age and older observed in Trials 1 and 2 [see Adverse Reactions (6.1)].

There is a risk of cataracts in pediatric patients treated with ALYFTREK. Perform baseline and follow-up ophthalmological examination in pediatric patients prior to and during treatment with ALYFTREK [see Warnings and Precautions (5.7)].

The safety and effectiveness of ALYFTREK in patients younger than 6 years of age have not been established.

Juvenile Animal Toxicity Data

Findings of cataracts were observed in juvenile rats dosed from postnatal Day 7 through 35 with ivacaftor dose levels of 10 mg/kg/day and higher (0.21 times the MRHD based on systemic exposure of ivacaftor and its metabolites). This finding has not been observed in older animals [see Warnings and Precautions (5.7)].

Studies were conducted with tezacaftor in juvenile rats starting at postnatal day (PND) 21 and ranging up to PNDs 35 to 49. Findings of convulsions and death were observed in juvenile rats that received a tezacaftor dose level of 100 mg/kg/day (approximately equivalent to 1.9 times the MRHD based on summed AUCs of tezacaftor and its metabolite, M1-TEZ). A no effect dose level was identified at 30 mg/kg/day (approximately equivalent to 0.8 times the MRHD based on summed AUCs of tezacaftor and its metabolite, M1-TEZ). Findings were dose related and generally more severe when dosing with tezacaftor was initiated earlier in the postnatal period (PND 7, which would be approximately equivalent to a human neonate). Tezacaftor and its metabolite, M1-TEZ, are substrates for P-glycoprotein. Lower brain levels of P-glycoprotein activity in younger rats resulted in higher brain levels of tezacaftor and M1-TEZ. These findings are not relevant for the indicated pediatric population 6 to 11 years of age, for whom levels of P-glycoprotein activity are equivalent to levels observed in adults.

8.5 Geriatric Use

Clinical studies of ALYFTREK did not include a sufficient number of patients with CF aged 65 years and older (n=2, 0.4% of patients treated with ALYFTREK in Trials 1 and 2) to determine whether they respond differently from younger adult patients with CF.

8.6 Renal Impairment

The recommended ALYFTREK dosage in patients with CF with mild to moderate renal impairment (RI) (eGFR 30 to < 90 mL/min/1.73 m^2) is the same in patients with CF with normal kidney function. Use of ALYFTREK in patients with CF with severe RI (eGFR <30 mL/min/1.73 m^2) or end-stage renal disease is recommended only if the benefits are expected to outweigh the risks.

No clinically significant differences in the pharmacokinetics of vanzacaftor, tezacaftor, or deutivacaftor were observed in patients with mild to moderate RI (eGFR 30 to <90 mL/min/1.73 m^2) [see Clinical Pharmacology (12.3)]. The effect of severe RI (eGFR <30 mL/min/1.73 m^2) on vanzacaftor, tezacaftor, or deutivacaftor pharmacokinetics is unknown [see Clinical Pharmacology (12.3)].

8.7 Hepatic Impairment

Severe Hepatic Impairment

ALYFTREK should not be used in patients with severe hepatic impairment (HI) (Child-Pugh Class C). ALYFTREK has not been studied in patients with CF with severe HI [see Warnings and Precautions (5.1) and Adverse Reactions (6.1)].

Moderate Hepatic Impairment

The use of ALYFTREK is not recommended in patients with moderate HI (Child-Pugh Class B). Use of ALYFTREK should only be considered in patients with HI when there is a clear medical need, and the benefit outweighs the risk. If used, the recommended dosage in patients with moderate HI is the same as for patients with normal hepatic function. Liver function tests should be closely monitored [see Dosage and Administration (2.2), Warnings and Precautions (5.1) and Adverse Reactions (6.1)].

Mild Hepatic Impairment

The recommended dosage of ALYFTREK in patients with mild HI (Child-Pugh Class A) is the same as in patients with normal hepatic function. Liver function tests should be closely monitored [see Warnings and Precautions (5.1) and Adverse Reactions (6.1)].

10 OVERDOSAGE

Treatment of overdosage consists of general supportive measures including monitoring of vital signs and observation of the clinical status.

11 DESCRIPTION

ALYFTREK (vanzacaftor, tezacaftor, and deutivacaftor tablets) are fixed-dose combination tablets for oral use available as:

- 10 mg of vanzacaftor (equivalent to 10.6 mg of vanzacaftor calcium dihydrate), 50 mg of tezacaftor, 125 mg of deutivacaftor or
- 4 mg of vanzacaftor (equivalent to 4.24 mg of vanzacaftor calcium dihydrate), 20 mg of tezacaftor, 50 mg of deutivacaftor.

The tablets contain the following inactive ingredients: croscarmellose sodium, hypromellose, hypromellose acetate succinate, magnesium stearate, microcrystalline cellulose, and sodium lauryl sulfate. The tablet film coating contains Brilliant Blue FCF aluminum lake/FD&C Blue #1, carmine, hydroxypropyl cellulose, hypromellose, iron oxide red, talc, and titanium dioxide.

The active ingredients of ALYFTREK are described below.

Vanzacaftor

Vanzacaftor is provided as a calcium salt. Vanzacaftor calcium dihydrate is a white solid that is practically insoluble in water (< 0.1 mg/mL). Its chemical name is calcium bis((14S)-8-[3-(2-{dispiro[2.0.2^4.1^3]heptan-7-yl}ethoxy)pyrazol-1-yl]-12,12-dimethyl-2,2,4-trioxo-2λ^6-thia-3,9,11,18,23-pentaazatetracyclo[17.3.1.1^11,14.0^5,10]tetracosa-1(23),5,7,9,19,21-hexaen-3-ide) dihydrate. Its molecular formula is C32H38N7O4S∙Ca0.5∙H2O and its molecular weight is 654.82. Vanzacaftor calcium dihydrate has the following structural formula:

Tezacaftor

Tezacaftor is a white to off-white solid that is practically insoluble in water (< 5 microgram/mL). Its chemical name is 1-(2,2-difluoro-2H-1,3-benzodioxol-5-yl)-N-{1-[(2R)-2,3-dihydroxypropyl]-6-fluoro-2-(1-hydroxy-2-methylpropan-2-yl)-1H-indol-5-yl}cyclopropane-1-carboxamide. Its molecular formula is C26H27N2F3O6 and its molecular weight is 520.50. Tezacaftor has the following structural formula:

Deutivacaftor

Deutivacaftor is a white to off-white solid that is practically insoluble in water (< 0.1 mg/mL). Pharmacologically, it is a CFTR potentiator. Its chemical name is N-(2-(tert-butyl)-5-hydroxy-4-(2-(methyl-d3)propan-2-yl-1,1,1,3,3,3-d6)phenyl)-4-oxo-1,4-dihydroquinoline-3-carboxamide. Its molecular formula is C24H19D9N2O3 and its molecular weight is 401.55. Deutivacaftor has the following structural formula:

12 CLINICAL PHARMACOLOGY

12.1 Mechanism of Action

Vanzacaftor and tezacaftor bind to different sites on the CFTR protein and have an additive effect in facilitating the cellular processing and trafficking of select mutant forms of CFTR (including F508del-CFTR) to increase the amount of CFTR protein delivered to the cell surface compared to either molecule alone. Deutivacaftor potentiates the channel open probability (or gating) of the CFTR protein at the cell surface.

The combined effect of vanzacaftor, tezacaftor and deutivacaftor is increased quantity and function of CFTR at the cell surface, resulting in increased CFTR activity as measured both by CFTR mediated chloride transport in vitro and by sweat chloride in patients with CF.

CFTR Chloride Transport Assay in Fischer Rat Thyroid Cells Expressing Mutant CFTR Protein

Effects of vanzacaftor/tezacaftor/deutivacaftor on chloride transport for mutant CFTR protein was determined in Ussing chamber electrophysiology studies using a panel of Fischer Rat Thyroid (FRT) cell lines stably expressing CFTR protein from individual mutations. Vanzacaftor/tezacaftor/deutivacaftor increased chloride transport in FRT cells expressing select CFTR mutations, as identified in Table 5.

The threshold that the treatment-induced increase in chloride transport must exceed for the mutant CFTR protein to be considered responsive is ≥10% of normal over baseline. This threshold was used because it is expected to predict clinical benefit. For individual mutations, the magnitude of the net change over baseline in CFTR-mediated chloride transport in vitro is not correlated with the magnitude of clinical response.

CFTR Chloride Transport Assay in Human Bronchial Epithelial Cells Expressing Mutant CFTR Protein

Homozygous and heterozygous N1303K- Human Bronchial Epithelial (HBE) cells showed greater chloride transport in the presence of vanzacaftor/tezacaftor/deutivacaftor than F508del/F508del-HBE cells treated with tezacaftor/ivacaftor which has shown clinical benefit in people homozygous for F508del.

Patient Selection

Select patients 6 years of age and older for treatment of CF with ALYFTREK based on the presence of at least one F508del mutation or another responsive mutation in the CFTR gene (see Table 5) [see Indications and Usage (1)].

Table 5 lists CFTR mutations responsive to ALYFTREK based on clinical response, and/or in vitro data in FRT or HBE cells, or based on extrapolation of efficacy [see Clinical Studies (14)].

Table 5: List of CFTR Gene Mutations Responsive to ALYFTREK
Based on Clinical Data [Clinical data is obtained from Trials 1 and 2.]
A455E | G551D | L1077P [This mutation is also predicted to be responsive by FRT assay with ALYFTREK.] | R352Q | S549N | V754M
D1152H | G85E | L206W | R75Q | S549R | W1098C
F508del | H1054D | M1101K | S1159F | S945L | W1282R
G1244E | I336K | R1066H | S1251N | V562I | Y563N
Based on in vitro Data [The N1303K mutation is predicted to be responsive only by HBE assay. All other mutations predicted to be responsive with in vitro data are supported by FRT assay.]
1507_1515del9 | E116Q | G424S | I556V | P140S | R334L | T1053I
2183A→G | E193K | G463V | I601F | P205S | R334Q | T1086I
3141del9 | E292K | G480C | I618T | P499A | R347H | T1246I
3195del6 | E403D | G480S | I807M | P5L | R347L | T1299I
3199del6 | E474K | G551A | I980K | P574H | R347P | T338I
546insCTA | E56K | G551S | K1060T | P67L | R352W | T351I
A1006E | E588V | G576A | K162E | P750L | R516G | T604I
A1067P | E60K | G576A;R668C [Complex/compound mutations where a single allele of the CFTR gene has multiple mutations; these exist independent of the presence of mutations on the other allele.] | K464E | P99L | R516S | V1153E
A1067T | E822K | G622D | L1011S | Q1100P | R553Q | V1240G
A107G | E92K | G628R | L102R | Q1291R | R555G | V1293G
A120T | F1016S | G91R | L1065P | Q1313K | R560S | V201M
A234D | F1052V | G970D | L1324P | Q237E | R560T | V232D
A309D | F1074L | G970S | L1335P | Q237H | R668C | V392G
A349V | F1099L | H1085P | L137P | Q359R | R709Q | V456A
A46D | F1107L | H1085R | L1480P | Q372H | R74Q | V456F
A554E | F191V | H1375P | L15P | Q452P | R74W | V520F
A559T | F200I | H139R | L165S | Q493R | R74W;D1270N | V603F
A559V | F311del | H199R | L320V | Q552P | R74W;V201M | W361R
A561E | F311L | H199Y | L333F | Q98R | R74W;V201M;D1270N | Y1014C
A613T | F508C | H609R | L333H | R1048G | R75L | Y1032C
A62P | F508C;S1251N | H620P | L346P | R1066C | R751L | Y109N
A72D | F575Y | H620Q | L441P | R1066L | R792G | Y161D
C491R | F587I | H939R | L453S | R1066M | R933G | Y161S
D110E | G1047R | H939R;H949L | L619S | R1070Q | S1045Y | Y301C
D110H | G1061R | I1027T | L967S | R1070W | S108F | Y569C
D1270N | G1069R | I105N | L997F | R1162L | S1118F | Y913C
D1445N | G1123R | I1139V | M1101R | R117C | S1159P
D192G | G1247R | I1234Vdel6aa | M1137V | R117C;G576A;R668C | S1235R
D443Y | G1249R | I125T | M150K | R117G | S1255P
D443Y;G576A;R668C | G126D | I1269N | M152V | R117H | S13F
D513G | G1349D | I331N | M265R | R117L | S341P
D565G | G149R | I1366N | M952I | R117P | S364P
D579G | G178E | I1398S | M952T | R1283M | S492F
D614G | G178R | I148N | N1088D | R1283S | S549I
D836Y | G194R | I148T | N1303I | R170H | S589N
D924N | G194V | I175V | N1303K | R258G | S737F
D979V | G27E | I502T | N186K | R297Q | S912L
D993Y | G27R | I506L | N187K | R31C | S977F
E116K | G314E | I506T | N418S | R31L | T1036N
Based on Extrapolation [Efficacy is extrapolated to certain non-canonical splice mutations because clinical trials in all mutations in this subgroup are infeasible and these mutations are not amenable to interrogation by FRT system.]
1341G→A | 2789+2insA | 3041-15T→G | 3849+10kbC→T | 3850-3T→G | 5T;TG13 | 711+3A→G
1898+3A→G | 2789+5G→A | 3272-26A→G | 3849+4A→G | 4005+2T→C | 621+3A→G | E831X
2752-26A→G | 296+28A→G | 3600G→A | 3849+40A→G | 5T;TG12

12.2 Pharmacodynamics

Effects on Sweat Chloride

- In patients with CF heterozygous for F508del and a CFTR mutation that results in a protein that is not responsive to ivacaftor or tezacaftor/ivacaftor [minimal function mutation] (Trial 1) the treatment difference of ALYFTREK compared to ELX/TEZ/IVA for mean absolute change in sweat chloride from baseline through Week 24 was -8.4 mmol/L (95% CI: -10.5, -6.3; P <0.0001).
- In patients with CF homozygous for the F508del mutation, heterozygous for the F508del mutation and either a gating or a residual function mutation, or at least one mutation responsive to ELX/TEZ/IVA with no F508del mutation (Trial 2), the treatment difference of ALYFTREK compared to ELX/TEZ/IVA for mean absolute change in sweat chloride from baseline through Week 24 was -2.8 mmol/L (95% CI: -4.7, -0.9; P = 0.0034).
- In an open-label trial in patients with CF aged 6 to less than 12 years with at least one mutation that is responsive to ELX/TEZ/IVA (Trial 3) [see Adverse Reactions (6.1)], the mean absolute change in sweat chloride from baseline through Week 24 was -8.6 mmol/L (95% CI: -11.0, -6.3).

The clinical relevance of these differences in sweat chloride has not been established in interventional clinical trials.

Cardiac Electrophysiology

At approximately 6 times the maximum recommended dose of vanzacaftor, clinically significant QTc interval prolongation was not observed. Similarly, in separate studies of tezacaftor and ivacaftor evaluating up to 3 times the respective maximum recommended doses, clinically significant QTc interval prolongation was not observed.

12.3 Pharmacokinetics

The pharmacokinetic parameters for vanzacaftor, tezacaftor, and deutivacaftor in patients with CF aged 12 years and older are provided in Table 6 as mean (SD) unless otherwise specified. No clinically significant differences in the pharmacokinetics of vanzacaftor, tezacaftor, and deutivacaftor were observed between healthy adult subjects and patients with CF.

Table 6: Pharmacokinetics Parameters of ALYFTREK Components
 | Vanzacaftor | Tezacaftor | Deutivacaftor
Exposure
Cmax,ss (mcg/mL) | 0.812 (0.344) | 6.77 (1.24) | 2.33 (0.637)
AUC0-24h,ss (mcg∙h/mL) | 18.6 (8.08) | 89.5 (28.0) | 39.0 (15.3)
Time to steady state | within 20 days | within 8 days | within 8 days
AUC Accumulation Ratio | 6.09 (1.81) | 1.92 (0.337) | 1.74 (0.497)
Absorption
Tmax [Median (range)] (hours) | 7.80 (3.70, 11.9) | 1.60 (1.40, 1.70) | 3.7 (2.7, 11.4)
Effect of food
AUCinf [When administered with fat-containing meals relative to fasted conditions. Note: The high-fat meal was approximately 800-1000 calories with 50% fat. The low-fat meal was approximately 400-500 calories with 25% fat.] | Increase 4- (low-fat meal) to 6- (high-fat meal) fold | No clinically significant change | Increase 3- (low-fat meal) to 4- (high-fat meal) fold
Distribution [Vanzacaftor, tezacaftor, deutivacaftor do not partition preferentially into human red blood cells.]
Apparent (oral) volume of distribution (L) | 121 (28.6) | 73.1 (13.3) | 159 (26.1)
Protein Binding [Vanzacaftor and deutivacaftor bind primarily to albumin and alpha 1-acid glycoprotein. Tezacaftor binds primarily to albumin.] | > 99% | Approximately 99% | > 99%
Elimination
Effective Half-life (hours) [The mean (SD) terminal half-lives of vanzacaftor, tezacaftor, and deutivacaftor are 54.0 (10.1) hours, 92.4 (23.1) hours and 17.3 (2.67) hours, respectively based on a single dose of vanzacaftor/tezacaftor/deutivacaftor tablets in healthy subjects in the fed state.] | 92.8 (30.2) | 22.5 (5.85) | 19.2 (8.71)
Apparent (oral) Clearance (L/hours) | 1.34 (0.819) | 1.22 (0.390) | 7.29 (2.68)
Metabolism
Primary Pathway | CYP3A4/5 | CYP3A4/5 | CYP3A4/5
Active metabolites | None | M1-TEZ | M1-D-IVA
Metabolite potency (relative to parent) | Not applicable | Similar | Approximately 20%
Excretion [Following radiolabeled doses.]
Feces | 91.6% (primarily metabolites) | 72% (unchanged or M2-TEZ) [0.79% as unchanged drug] | Not available
Urine | 0.50% | 13.7% | Not available
Abbreviations: AUC: area under the concentration versus time curve; SD: Standard Deviation; Cmax: maximum observed concentration; Tmax: time of maximum concentration; ss: steady state

Specific Populations

No clinically significant differences in the pharmacokinetics of vanzacaftor, tezacaftor, or deutivacaftor were observed based on age, sex, race, CFTR genotype, or mild to moderate renal impairment (eGFR 30 to <90 mL/min/1.73m^2 as estimated by modification of diet in renal disease (MDRD) equation). The effect of severe renal impairment (eGFR less than 30 mL/min/1.73m^2) on vanzacaftor, tezacaftor, or deutivacaftor pharmacokinetics is unknown.

Weight was identified as the key covariate having a clinically meaningful impact on pharmacokinetics of vanzacaftor, tezacaftor, and deutivacaftor.

Pediatric Patients Aged 6 to Less Than 18 Years

Vanzacaftor, tezacaftor and deutivacaftor exposures observed in clinical trials are presented by age group and dosage administered in Table 7. No clinically significant differences in vanzacaftor, tezacaftor, and deutivacaftor exposures were observed in patients with CF aged 6 to less than 18 years compared to adults following the recommended dosages.

Table 7: Mean (SD) Vanzacaftor, Tezacaftor and Deutivacaftor Exposures by Age Group
Age Group | Weight | Dosage (once daily) | AUC0-24h (mcg∙h/mL)
Age Group | Weight | Dosage (once daily) | Vanzacaftor | Tezacaftor | Deutivacaftor
6 to <12 years | <40 kg (N = 70) | vanzacaftor 12 mg tezacaftor 60 mg deutivacaftor 150 mg | 13.0 (4.90) | 69.1 (20.7) | 30.2 (11.6)
6 to <12 years | ≥40 kg (N = 8) | vanzacaftor 20 mg tezacaftor 100 mg deutivacaftor 250 mg | 18.6 (7.49) | 101 (33.7) | 48.5 (18.7)
12 to <18 years | - (N = 66) | vanzacaftor 20 mg tezacaftor 100 mg deutivacaftor 250 mg | 15.8 (6.52) | 93.0 (32.5) | 37.1 (15.3)
≥18 years | - (N = 414) | vanzacaftor 20 mg tezacaftor 100 mg deutivacaftor 250 mg | 19.0 (8.22) | 89.0 (27.2) | 39.3 (15.3)
Abbreviations: SD: Standard Deviation; AUC0-24h: Area Under the Concentration versus time curve at steady state

Patients with Hepatic Impairment

Vanzacaftor AUC was approximately 30% lower, tezacaftor AUC was comparable, and deutivacaftor AUC was approximately 20% lower in subjects with moderate hepatic impairment (Child-Pugh Class B) compared to subjects with normal liver function matched for demographics [see Use in Specific Populations (8.7)].

The effect of mild hepatic impairment (Child-Pugh Class A) or severe hepatic impairment (Child-Pugh Class C) on vanzacaftor, tezacaftor, or deutivacaftor pharmacokinetics is unknown.

Drug Interaction Studies

Clinical Studies and Model-Informed Approaches

Exposure changes associated with concomitant use of vanzacaftor, tezacaftor, ivacaftor and/or deutivacaftor with other drugs are shown in Table 8.

Table 8: Observed or Predicted Exposure Changes Associated with Concomitant Use of Vanzacaftor, Tezacaftor, Ivacaftor and/or Deutivacaftor with Other Drugs
Dosage |  | Effected Drug | Geometric Mean Ratio (90% CI) No Effect = 1.0
Dosage |  | Effected Drug | AUC | Cmax
Itraconazole 200 mg q12h on Day 1, followed by 200 mg daily | TEZ 25 mg daily + IVA 50 mg daily | Tezacaftor | 4.02 (3.71, 4.63) | 2.83 (2.62, 3.07)
Itraconazole 200 mg daily | ELX 20 mg + TEZ 50 mg + D-IVA 50 mg single dose | Tezacaftor | 4.51 (3.85, 5.29) | 1.48 (1.33, 1.65)
Itraconazole 200 mg daily | ELX 20 mg + TEZ 50 mg + D-IVA 50 mg single dose | Deutivacaftor | 11.1 (8.72, 14.1) | 1.96 (1.70, 2.26)
Itraconazole 200 mg daily [The itraconazole dosing (200 mg qd for14 days) did not fully cover the elimination of vanzacaftor. A 10.5-fold increase in vanzacaftor AUC is predicted by physiologically based pharmacokinetic modeling and simulations when itraconazole fully covers the elimination.] | VNZ 5 mg single dose | Vanzacaftor | 6.37 (5.53, 7.35) | 1.55 (1.41, 1.70)
Ciprofloxacin [Effect is not clinically significant [see Drug Interactions (7.3)].] 750 mg twice daily | TEZ 50 mg q12h + IVA 150 mg q12h | Tezacaftor | 1.08 (1.03, 1.13) | 1.05 (0.99, 1.11)
Digoxin 0.5 mg single dose | TEZ 25 mg daily + IVA 50 mg daily | Digoxin | 1.3 (1.17, 1.45) | 1.32 (1.07, 1.64)
Fluconazole 200 mg daily | VNZ 20 mg qd + TEZ 100 mg + D-IVA 250 mg qd | Vanzacaftor | 2.55 (2.12, 3.12) [Predicted by physiologically based pharmacokinetic modeling and simulations. Data presented as geometric mean ratio and 5th to 95th percentiles of individuals in the simulated population [see Drug Interactions (7.1)].] | 2.48 (2.04, 3.01)
Fluconazole 200 mg daily | VNZ 20 mg qd + TEZ 100 mg + D-IVA 250 mg qd | Deutivacaftor | 3.13 (2.44, 3.95) | 2.27 (1.82, 2.93)
Erythromycin 500 mg four times daily | VNZ 20 mg qd + TEZ 100 mg + D-IVA 250 mg qd | Vanzacaftor | 3.29 (1.62, 7.55) | 3.19 (1.60, 7.29)
Erythromycin 500 mg four times daily | VNZ 20 mg qd + TEZ 100 mg + D-IVA 250 mg qd | Deutivacaftor | 4.13 (1.80, 9.73) | 2.89 (1.52, 6.97)
Verapamil 80 mg three times daily | VNZ 20 mg qd + TEZ 100 mg + D-IVA 250 mg qd | Vanzacaftor | 3.93 (1.84, 8.75) | 3.80 (1.78, 8.33)
Verapamil 80 mg three times daily | VNZ 20 mg qd + TEZ 100 mg + D-IVA 250 mg qd | Deutivacaftor | 5.11 (2.06, 12.5) | 3.43 (1.64, 7.65)
Rifampin 600 mg daily | VNZ 20 mg qd + TEZ 100 mg + D-IVA 250 mg qd | Vanzacaftor | 0.18 (0.10, 0.34) | 0.22 (0.12, 0.38)
Rifampin 600 mg daily | VNZ 20 mg qd + TEZ 100 mg + D-IVA 250 mg qd | Deutivacaftor | 0.10 (0.04, 0.26) | 0.20 (0.08, 0.44)
Carbamazepine 400 mg twice daily | VNZ 20 mg qd + TEZ 100 mg + D-IVA 250 mg qd | Vanzacaftor | 0.44 (0.28, 0.61) | 0.46 (0.31, 0.64)
Carbamazepine 400 mg twice daily | VNZ 20 mg qd + TEZ 100 mg + D-IVA 250 mg qd | Deutivacaftor | 0.24 (0.11, 0.47) | 0.32 (0.17, 0.57)
Efavirenz 600 mg daily | VNZ 20 mg qd + TEZ 100 mg + D-IVA 250 mg qd | Vanzacaftor | 0.31 (0.16, 0.57) | 0.35 (0.19, 0.59)
Efavirenz 600 mg daily | VNZ 20 mg qd + TEZ 100 mg + D-IVA 250 mg qd | Deutivacaftor | 0.27 (0.11, 0.50) | 0.44 (0.23, 0.68)
Abbreviations: CI = Confidence Interval; ELX = elexacaftor; VNZ = vanzacaftor; TEZ = tezacaftor; IVA = ivacaftor; D-IVA = deutivacaftor; PK = Pharmacokinetics; qd = once daily

Other Drugs: No clinically significant differences in tezacaftor pharmacokinetics were observed when tezacaftor/ivacaftor was used concomitantly with ciprofloxacin. No clinically significant differences in the pharmacokinetics of the following drugs were observed when used concomitantly with tezacaftor/ivacaftor: midazolam (CYP3A4 substrate) or ethinyl estradiol/norethindrone containing hormonal contraceptives.

In Vitro Studies

CYP450 Enzymes: Vanzacaftor, tezacaftor, and deutivacaftor are CYP3A substrates. Deutivacaftor inhibits CYP2C8, CYP2C9, and CYP3A4. Vanzacaftor and tezacaftor do not inhibit CYP1A2, CYP2B6, CYP2C8, CYP2C9, CYP2C19, CYP2D6, and CYP3A4. Vanzacaftor, tezacaftor, and deutivacaftor do not induce CYP3A4.

Transporter Systems: Tezacaftor and deutivacaftor are substrates of P-gp, but vanzacaftor is not a substrate of P-gp. Tezacaftor is a substrate of BCRP, OATP1B1, but not OATP1B3. Vanzacaftor and deutivacaftor are not substrates for OATP1B1 or OATP1B3. Vanzacaftor and deutivacaftor are BCRP inhibitors. Vanzacaftor, tezacaftor and deutivacaftor are P-gp inhibitors. Vanzacaftor, tezacaftor, and deutivacaftor do not inhibit OATP1B1 nor OATP1B3.

13 NONCLINICAL TOXICOLOGY

13.1 Carcinogenesis, Mutagenesis, Impairment of Fertility

No studies of carcinogenicity, mutagenicity, or impairment of fertility were conducted with the combination of vanzacaftor, tezacaftor, and deutivacaftor; however, separate studies of vanzacaftor, tezacaftor, deutivacaftor, and ivacaftor are described below.

Vanzacaftor

A 6-month study in Tg.rasH2 mice showed no evidence of tumorigenicity at 30 mg/kg/day dose, the highest dose tested.

Vanzacaftor was negative for genotoxicity in the following assays: Ames test for bacterial gene mutation, in vitro micronucleus assay in TK6 cells, and in vivo rat micronucleus assay.

Administration of oral vanzacaftor had no effects on fertility and early embryonic development in male and female rats at up to 12.5 and 10 mg/kg/day, respectively (approximately 19 times for males and 30 times for females the exposure at the MRHD based on AUCs of vanzacaftor).

Tezacaftor

A two-year study in Sprague-Dawley rats and a 6-month study in Tg.rasH2 transgenic mice were conducted to assess the carcinogenic potential of tezacaftor. No evidence of tumorigenicity from tezacaftor was observed in male and female rats at oral doses up to 50 and 75 mg/kg/day (approximately 2 and 4 times the MRHD based on summed AUCs of tezacaftor and M1-TEZ in males and females, respectively). No evidence of tumorigenicity was observed in male and female Tg.rasH2 transgenic mice at tezacaftor doses up to 500 mg/kg/day.

Tezacaftor was negative for genotoxicity in the following assays: Ames test for bacterial gene mutation, in vitro chromosomal aberration assay in Chinese hamster ovary cells and in vivo mouse micronucleus test.

There were no effects on male or female fertility and early embryonic development in rats at oral tezacaftor doses up to 100 mg/kg/day (approximately 3 times the MRHD based on summed AUC of tezacaftor and M1-TEZ).

Deutivacaftor

Deutivacaftor is a deuterated isotopologue of ivacaftor with an established toxicity profile similar to ivacaftor based on a 13-week single-agent repeat dose toxicity study; therefore, reproductive and developmental toxicity data and carcinogenicity data from ivacaftor are expected to be equivalent to deutivacaftor.

Ivacaftor

Two-year studies were conducted in CD-1 mice and Sprague-Dawley rats to assess the carcinogenic potential of ivacaftor. No evidence of tumorigenicity from ivacaftor was observed in mice or rats at oral doses up to 200 mg/kg/day and 50 mg/kg/day, respectively (approximately equivalent to 3 and 11 times the MRHD, respectively, based on summed AUCs of ivacaftor).

Ivacaftor was negative for genotoxicity in the following assays: Ames test for bacterial gene mutation, in vitro chromosomal aberration assay in Chinese hamster ovary cells and in vivo mouse micronucleus test.

Ivacaftor impaired fertility and reproductive performance indices in male and female rats at 200 mg/kg/day (approximately 15 and 13 times, respectively, the MRHD based on AUCs of ivacaftor). Increases in prolonged diestrus were observed in females at 200 mg/kg/day. Ivacaftor also increased the number of females with all nonviable embryos and decreased corpora lutea, implantations and viable embryos in rats at 200 mg/kg/day when dams were dosed prior to and during early pregnancy. Slight decreases of the seminal vesicle weights were observed in males at 200 mg/kg/day dose (approximately 15 times the MRHD based on summed AUCs of ivacaftor). These impairments of fertility and reproductive performance in male and female rats at 200 mg/kg/day were attributed to severe toxicity.

14 CLINICAL STUDIES

The efficacy of ALYFTREK in patients aged 12 years and older with cystic fibrosis (CF) who have at least one F508del mutation or a responsive mutation in the CFTR gene was evaluated in two 52-week randomized, double-blind, active-controlled trials comparing ALYFTREK and a fixed-dose combination drug containing elexacaftor, tezacaftor, and ivacaftor (ELX/TEZ/IVA) (Trial 1, NCT05033080 and Trial 2, NCT05076149). The two trials enrolled a total of 971 patients aged 12 years and older with CF who have at least one F508del mutation or other ELX/TEZ/IVA-responsive mutations in the CFTR gene. Because patients in Trial 1 and Trial 2 would receive ELX/TEZ/IVA, patients with a history of intolerance to ELX/TEZ/IVA were excluded from these trials.

- Trial 1 enrolled patients with CF heterozygous for F508del and a CFTR mutation that results in a protein that was not responsive to ivacaftor or tezacaftor/ivacaftor (minimal function mutation). A total of 398 patients with CF aged 12 years and older received a daily oral dosage of ELX/TEZ/IVA (elexacaftor 200 mg/tezacaftor 100 mg/ivacaftor 150 mg in the morning and ivacaftor 150 mg in the evening) during a 4-week run-in period and were then randomized to receive ALYFTREK (total once daily oral dosage of vanzacaftor 20 mg/tezacaftor 100 mg/deutivacaftor 250 mg) or ELX/TEZ/IVA (same dosage as in the run-in period) during the 52-week treatment period. Patients had a mean age of 30.8 years (range: 12.2 to 71.6 years), were 59% male, 97.5% White, 1.3% Black/African American, 0.3% Asian, 0.3% Other race, and 6% Hispanic or Latino ethnicity. After the 4₋week run-in, the mean ppFEV1 at baseline was 67.1 percentage points (range: 28.0, 108.6) and the mean sweat chloride at baseline was 53.9 mmol/L (range: 10.0 mmol/L, 113.5 mmol/L).
- Trial 2 enrolled patients with CF who had one of the following genotypes: homozygous for the F508del mutation, heterozygous for the F508del mutation and either a gating or a residual function mutation, or at least one mutation responsive to ELX/TEZ/IVA with no F508del mutation. A total of 573 patients with CF aged 12 years and older received a daily oral dosage of ELX/TEZ/IVA (elexacaftor 200 mg/tezacaftor 100 mg/ivacaftor 150 mg in the morning and ivacaftor 150 mg in the evening) during a 4-week run-in period and were then randomized to receive ALYFTREK (total once daily oral dosage of vanzacaftor 20 mg/tezacaftor 100 mg/ deutivacaftor 250 mg) or ELX/TEZ/IVA (same dosage as during the run-in period) during the 52-week treatment period. Patients had a mean age of 33.7 years (range: 12.2 to 71.2 years), were 51.1% male, 92.8% White, 0% Black/African American, 0.3% Asian, 0.2% American Indian or Alaska Native, 0.3% Other race, and 1.6% Hispanic or Latino ethnicity. After the 4-week run-in, the mean ppFEV1 at baseline was 66.8 percentage points (range: 36.4, 112.5) and the mean sweat chloride at baseline was 42.8 mmol/L (range: 10.0 mmol/L, 113.3 mmol/L).

Efficacy Endpoints

In both trials, the primary endpoint evaluated non-inferiority in mean absolute change in ppFEV1 from baseline through Week 24 and a key secondary endpoint evaluated the mean absolute change from baseline in sweat chloride through Week 24 in the ALYFTREK and ELX/TEZ/IVA treatment groups.

Trials 1 and 2 also assessed other secondary endpoints including pulmonary exacerbation rate and change in Cystic Fibrosis Questionnaire-Revised respiratory domain (CFQ-R RD) score from baseline.

Efficacy Results

- In Trial 1, treatment with ALYFTREK resulted in an LS mean difference of 0.2 percentage points (95% CI: -0.7, 1.1) in absolute change in ppFEV1 from baseline through Week 24 compared to ELX/TEZ/IVA.
- In Trial 2, treatment with ALYFTREK resulted in an LS mean difference of 0.2 percentage points (95% CI: -0.5, 0.9) in absolute change in ppFEV1 from baseline through Week 24 compared to ELX/TEZ/IVA.

As the lower bounds of the 95% CI of the LS mean difference in absolute change from baseline in ppFEV1 through Week 24 were greater than -3.0 percentage points (the pre-specified non-inferiority margin) in Trial 1 and Trial 2, these results demonstrate non-inferiority of ALYFTREK to ELX/TEZ/IVA.

Table 9 provides the primary and key secondary efficacy endpoints results for Trials 1 and 2.

Table 9: Efficacy Results in Patients Aged 12 Years and Older with CF Who Had at Least One F508del Mutation or Responsive Mutation in the CFTR Gene (Trials 1 and 2)
Analysis [A 4-week ELX/TEZ/IVA run-in-period was performed to establish an on-treatment baseline.] | Statistic | Trial 1 |  | Trial 2
Analysis [A 4-week ELX/TEZ/IVA run-in-period was performed to establish an on-treatment baseline.] | Statistic | ALYFTREK N = 196 | ELX/TEZ/IVA N = 202 | ALYFTREK N = 284 | ELX/TEZ/IVA N = 289
Primary Endpoint
Absolute change from baseline in ppFEV1 through Week 24 (percentage points) | n | 187 | 193 | 268 | 276
Absolute change from baseline in ppFEV1 through Week 24 (percentage points) | LS mean (SE) | 0.5 (0.3) | 0.3 (0.3) | 0.2 (0.3) | 0.0 (0.2)
Absolute change from baseline in ppFEV1 through Week 24 (percentage points) | LS mean difference, 95% CI [The pre-specified non-inferiority margin was -3.0 percentage points.] | 0.2 (-0.7, 1.1) |  | 0.2 (-0.5, 0.9)
Key Secondary Endpoint
Absolute change from baseline in SwCl through Week 24 (mmol/L) | n | 185 | 194 | 270 | 276
Absolute change from baseline in SwCl through Week 24 (mmol/L) | LS mean (SE) | -7.5 (0.8) | 0.9 (0.8) | -5.1 (0.7) | -2.3 (0.7)
Absolute change from baseline in SwCl through Week 24 (mmol/L) | LS mean difference, 95% CI | -8.4 (-10.5, -6.3) |  | -2.8 (-4.7, -0.9)
Absolute change from baseline in SwCl through Week 24 (mmol/L) | P-value (2-sided) | < 0.0001 |  | 0.0034
ppFEV1: percent predicted Forced Expiratory Volume in 1 second; CI: Confidence Interval; SE: Standard Error; SwCl: sweat chloride
Note: Analyses were based on the full analysis set (FAS). FAS was defined as all randomized subjects who carry the intended CFTR allele mutation and received at least 1 dose of study drug.

The trials were not designed to demonstrate a difference between the treatment groups or to support non-inferiority of the other secondary endpoints. In Trial 1 and Trial 2, mean absolute change from baseline ppFEV1 through Week 52, the rate in pulmonary exacerbations through Week 52, and the absolute change from baseline in the CFQ-R RD through Week 24 were similar between the ALYFTREK-treated and the ELX/TEZ/IVA-treated patients. The results were not tested for statistical significance as they were not in the pre-specified multiple testing procedure.

16 HOW SUPPLIED/STORAGE AND HANDLING

ALYFTREK (vanzacaftor, tezacaftor, and deutivacaftor) tablets are supplied as follows:

Table 10: ALYFTREK Tablets and Package Configuration
Strengths | Tablet Description | Package Configuration | NDC
4 mg of vanzacaftor/ 20 mg of tezacaftor / 50 mg of deutivacaftor | purple, round-shaped, film-coated, debossed with "V4" on one side and plain on the other | 84-count carton containing 4 wallets, each wallet containing 21 tablets in blister packs | NDC 51167-135-01
10 mg of vanzacaftor/ 50 mg of tezacaftor / 125 mg of deutivacaftor | purple, oblong-shaped, film-coated, debossed with "V10" on one side and plain on the other | 56-count carton containing 4 wallets, each wallet containing 14 tablets in blister packs | NDC 51167-121-01

STORAGE AND HANDLING

Store at 20°C - 25°C (68°F - 77°F); excursions permitted to 15°C - 30°C (59°F - 86°F) [see USP Controlled Room Temperature].

17 PATIENT COUNSELING INFORMATION

Advise the patient to read the FDA-approved patient labeling (Medication Guide).

Drug-Induced Liver Injury and Liver Failure

Inform patients that elevations of transaminases have occurred in patients with CF treated with ALYFTREK and that cases of drug-induced liver injury and failure have been observed with fixed-dose combination drug containing elexacaftor, tezacaftor, and ivacaftor, which contains the same or similar active ingredients as ALYFTREK.

Advise all patients that liver function tests should be assessed prior to initiating ALYFTREK, and then assessed every month during the first 6 months of treatment, then every 3 months for the next 12 months, then at least annually thereafter. Inform patients with a history of liver disease or liver function test elevations at baseline that more frequent monitoring may be necessary. Instruct patients to interrupt treatment with ALYFTREK if symptoms of liver injury occur (e.g., jaundice, right upper quadrant pain, nausea, vomiting, altered mental status, ascites) and notify their healthcare provider immediately [see Dosage and Administration (2.1), Warnings and Precautions (5.1), Adverse Reactions (6.1), Use in Specific Populations (8.7) and Clinical Pharmacology (12.3)].

Hypersensitivity Reactions, Including Anaphylaxis

Inform patients that hypersensitivity reactions including anaphylaxis have been reported in patients who received drugs containing elexacaftor, tezacaftor, and/or ivacaftor (the same or similar active ingredients as ALYFTREK). Instruct patients to discontinue ALYFTREK and notify their healthcare provider if they experience signs and symptoms of a hypersensitivity reaction, including rash, hives, itching, facial swelling, tightness of the chest and wheezing [see Warnings and Precautions (5.2)].

Patients Who Discontinued or Interrupted Elexacaftor-, Tezacaftor-, or Ivacaftor-Containing Drugs Due to Adverse Reactions

Inform patients that there is no available safety data for ALYFTREK in patients who previously discontinued or interrupted treatment with elexacaftor-, tezacaftor-, or ivacaftor-containing drugs due to adverse reactions. These patients who start treatment with ALYFTREK may require closer and more frequent monitoring [see Warnings and Precautions (5.3)].

Intracranial Hypertension

Inform patients that intracranial hypertension has occurred in patients who received drugs containing the same or similar active ingredients as ALYFTREK. Instruct patients to notify their healthcare provider right away if they experience signs and symptoms of intracranial hypertension, including headache, blurred vision, diplopia, and vision loss [see Warnings and Precautions (5.4)].

Drug Interactions with CYP3A Inducers and Inhibitors

Inform patients that certain medications, herbal supplements, or vitamins, when used concomitantly with ALYFTREK, may reduce the effectiveness of ALYFTREK or increase the risk of adverse reactions associated with ALYFTREK. Instruct patients to report all concomitant medications, herbal supplements, or vitamins, to their healthcare providers while taking ALYFTREK [see Dosage and Administration (2.3), Warnings and Precautions (5.5, 5.6) and Drug Interactions (7.1)].

Instruct patients to avoid food or drink containing grapefruit when using ALYFTREK [see Drug Interactions (7.1)].

Cataracts

Inform patients that abnormality of the eye lens (cataract) has been noted in some pediatric patients receiving drugs containing ivacaftor (which is similar to an active ingredient in ALYFTREK) and baseline and follow-up ophthalmological examinations are needed in pediatric patients receiving ALYFTREK [see Warnings and Precautions (5.7) and Nonclinical Toxicology (13.1)].

Administration

Inform patients that ALYFTREK is best absorbed by the body when taken with food that contains fat. Examples include eggs, butter, peanut butter, whole-milk dairy products (such as whole milk, cheese and yogurt), etc. [see Dosage and Administration (2.2) and Clinical Pharmacology (12.3)].

Inform patients of the following if they miss an ALYFTREK dose [see Dosage and Administration (2.5)]:

- If 6 hours or less have passed since the missed dose is usually taken, patients with CF should be instructed to take the prescribed dose with fat-containing food as soon as possible.
- If more than 6 hours have passed since the missed dose, patients with CF should be instructed to skip the missed dose and continue on the original schedule the next day.

Manufactured for
Vertex Pharmaceuticals Incorporated
50 Northern Avenue
Boston, MA 02210

ALYFTREK, VERTEX and associated logos are trademarks of Vertex Pharmaceuticals Incorporated.
All other trademarks referenced herein are the property of their respective owners.
©2025 Vertex Pharmaceuticals Incorporated
All Rights Reserved

MEDICATION GUIDE
ALYFTREK™ (ah-LIF-trek)
(vanzacaftor, tezacaftor, and deutivacaftor tablets), tablets for oral use

What is the most important information I should know about ALYFTREK?

Elevated liver enzymes have been observed in patients taking ALYFTREK. Cases of serious liver damage and liver failure leading to transplantation and death have been seen in some people with or without a history of liver problems taking elexacaftor/tezacaftor/ivacaftor (TRIKAFTA®), a medicine which has the same or similar active ingredients as ALYFTREK.

Your healthcare provider will do blood tests to check your liver:

- before you start ALYFTREK
- every month during your first 6 months of taking ALYFTREK
- then every 3 months during the next 12 months of taking ALYFTREK
- then at least every year while you are taking ALYFTREK

Your healthcare provider may do blood tests to check the liver more often if you have had high liver enzymes in your blood in the past or are experiencing signs or symptoms of liver injury.
Stop taking ALYFTREK and call your healthcare provider right away if you have any of the following symptoms of liver problems:

- pain, swelling, or discomfort in the upper right stomach (abdominal) area
- yellowing of your skin or the white part of your eyes
- mental changes

- nausea or vomiting
- dark, amber-colored urine
- loss of appetite
- have fluid in your stomach area (ascites)

What is ALYFTREK?

- ALYFTREK is a prescription medicine used for the treatment of cystic fibrosis (CF) in people aged 6 years and older who have at least one F508del mutation or another responsive mutation in the cystic fibrosis transmembrane conductance regulator (CFTR) gene.
- Talk to your healthcare provider to learn if you have an indicated CF gene mutation.

It is not known if ALYFTREK is safe and effective in children under 6 years of age.

What should I tell my healthcare provider before taking ALYFTREK?

Before taking ALYFTREK, tell your healthcare provider about all of your medical conditions, including if you:

- have or have had liver problems.
- are allergic to ALYFTREK or any ingredients in ALYFTREK. See the end of this medication guide for a complete list of ingredients in ALYFTREK.
- have taken another medicine with elexacaftor, tezacaftor, or ivacaftor before and temporarily or permanently stopped because of side effects. Your healthcare provider may want to see you more often.
- have kidney problems.
- are pregnant or plan to become pregnant. It is not known if ALYFTREK will harm your unborn baby. You and your healthcare provider should decide if you will take ALYFTREK while you are pregnant.
- are breastfeeding or planning to breastfeed. It is not known if ALYFTREK passes into your breast milk. You and your healthcare provider should decide if you will take ALYFTREK while you are breastfeeding.

Tell your healthcare provider about all the medicines you take, including prescription and over-the-counter medicines, vitamins, and herbal supplements.

ALYFTREK may affect the way other medicines work and other medicines may affect how ALYFTREK works.

The dose of ALYFTREK may need to be adjusted when taken with certain medicines. Ask your healthcare provider or pharmacist for a list of these medicines if you are not sure.

Know the medicines you take. Keep a list of them to show your healthcare provider and pharmacist when you get a new medicine.

How should I take ALYFTREK?

- Take ALYFTREK exactly as your healthcare provider tells you to take it.
- Take ALYFTREK by mouth only.
- Always take ALYFTREK tablets with food that contains fat. Examples of fat-containing foods include butter, oil, eggs, peanut butter, nuts, meat, and whole-milk dairy products such as whole milk, cheese, and yogurt.
- ALYFTREK tablets (age 6 to less than 12 years weighing less than 88 pounds (40 kg)):
  - The purple round-shaped tablet is marked with 'V4' and each tablet contains the medicines vanzacaftor, tezacaftor, and deutivacaftor. Take 3 tablets at the same time each day.
- ALYFTREK tablets (age 6 to less than 12 years weighing 88 pounds (40 kg) or more, or 12 years and older):
  - The purple oblong-shaped tablet is marked with 'V10' and each tablet contains the medicines vanzacaftor, tezacaftor, and deutivacaftor. Take 2 tablets at the same time each day.
- Take ALYFTREK tablets whole.
- Take the doses about the same time every day.
- If you miss a dose of ALYFTREK and:
  - it is 6 hours or less from the time you usually take the dose, take the missed dose with food that contains fat as soon as you can. Then take your next dose at your usual time.
  - it is more than 6 hours from the time you usually take the dose, do not take the missed dose. Take your dose the next day at your usual time.
  - Do not take more than your usual dose of ALYFTREK to make up for a missed dose.

If you are not sure about your dosing, call your healthcare provider.

What should I avoid while taking ALYFTREK?

Avoid food or drink that contains grapefruit while you are taking ALYFTREK.

What are the possible or reasonably likely side effects of ALYFTREK?

ALYFTREK can cause serious side effects, including:

- See "What is the most important information I should know about ALYFTREK?"
- Serious Allergic Reactions can happen to people who are treated with ALYFTREK. Call your healthcare provider or go to the emergency room right away if you have any symptoms of an allergic reaction. Symptoms of an allergic reaction may include:
  - rash or hives
  - tightness of the chest or throat or difficulty breathing
  - light-headedness or dizziness
- Increased pressure around the brain (intracranial hypertension) has happened in people treated with medicines containing the same or similar ingredients as ALYFTREK. If you experience an unusual headache, blurred vision, double vision, or vision loss, call your healthcare provider right away.
- Abnormality of the eye lens (cataract) has happened in some children and adolescents treated with ALYFTREK. If you are a child or adolescent, your healthcare provider should perform eye examinations before and during treatment with ALYFTREK to look for cataracts.

The most common side effects of ALYFTREK include:

- cough
- pain or swelling of your nose or throat (nasopharyngitis)
- upper respiratory tract infection (common cold) including stuffy and runny nose
- headache

- mouth or throat pain
- flu (influenza)
- tiredness
- increase in liver enzymes
- rash
- sinus congestion

Your healthcare provider should monitor you during treatment with ALYFTREK. You may require additional monitoring if your treatment with a medicine that works like ALYFTREK has been previously stopped or interrupted because of side effects.

Tell your healthcare provider if you have any side effect that bothers you or that does not go away.
These are not all of the possible side effects of ALYFTREK. For more information, ask your healthcare provider or pharmacist.

Call your doctor for medical advice about side effects. You may report side effects to FDA at 1-800-FDA-1088.

How should I store ALYFTREK?

- Store ALYFTREK at room temperature between 68°F to 77°F (20°C to 25°C).

Keep ALYFTREK and all medicines out of the reach of children.

General information about the safe and effective use of ALYFTREK.

Medicines are sometimes prescribed for purposes other than those listed in a Medication Guide. Do not use ALYFTREK for a condition for which it was not prescribed. Do not give ALYFTREK to other people, even if they have the same symptoms that you have. It may harm them.

You can ask your pharmacist or healthcare provider for information about ALYFTREK that is written for health professionals.

What are the ingredients in ALYFTREK?

Active ingredients: vanzacaftor, tezacaftor, and deutivacaftor.

Inactive ingredients: croscarmellose sodium, hypromellose, hypromellose acetate succinate, magnesium stearate, microcrystalline cellulose, and sodium lauryl sulfate. The tablet film coat contains Brilliant Blue FCF aluminum lake/FD&C Blue #1, carmine, hydroxypropyl cellulose, hypromellose, iron oxide red, talc, and titanium dioxide.

Manufactured for: Vertex Pharmaceuticals Incorporated; 50 Northern Avenue, Boston, MA 02210
ALYFTREK, VERTEX and associated logos are trademarks of Vertex Pharmaceuticals Incorporated.
All other trademarks referenced herein are the property of their respective owners.
©2025 Vertex Pharmaceuticals Incorporated
For more information, go to www.alyftrek.com or call 1-877-752-5933.

This Medication Guide has been approved by the U.S. Food and Drug Administration.

Revised: 09/2025

PRINCIPAL DISPLAY PANEL - 4 mg/20 mg/50 mg Tablet Wallet Carton

Rx Only
NDC 51167-135-01

84 tablets
4-wallets
(each containing
21 tablets)

alyftrek™
(vanzacaftor/tezacaftor/deutivacaftor)
tablets

4 mg/20 mg/50 mg
per tablet

ATTENTION PHARMACIST: Dispense enclosed Medication Guide to each patient.

Lift to open

PRINCIPAL DISPLAY PANEL - 10 mg/50 mg/125 mg Tablet Wallet Carton

Rx Only
NDC 51167-121-01

56 tablets
4-wallets
(each containing
14 tablets)

alyftrek™
(vanzacaftor/tezacaftor/deutivacaftor)
tablets

10 mg/50 mg/125 mg
per tablet

ATTENTION PHARMACIST: Dispense enclosed Medication Guide to each patient.

Lift to open